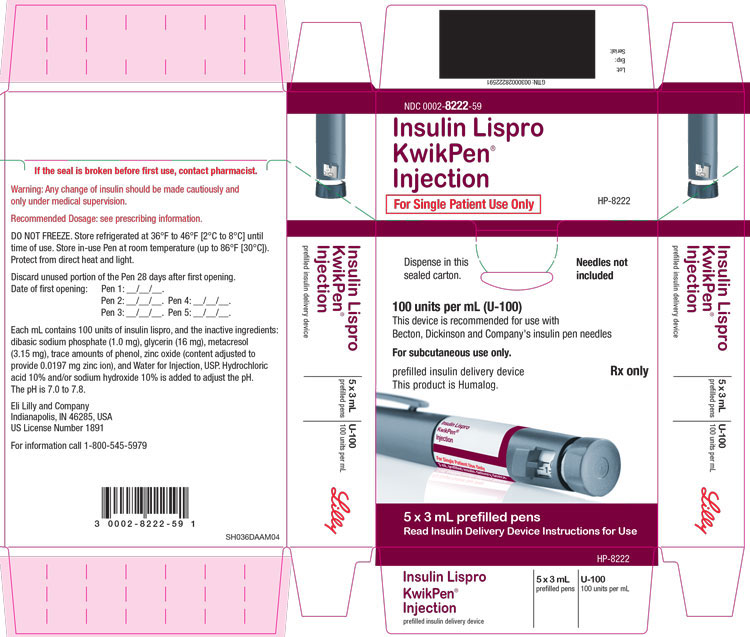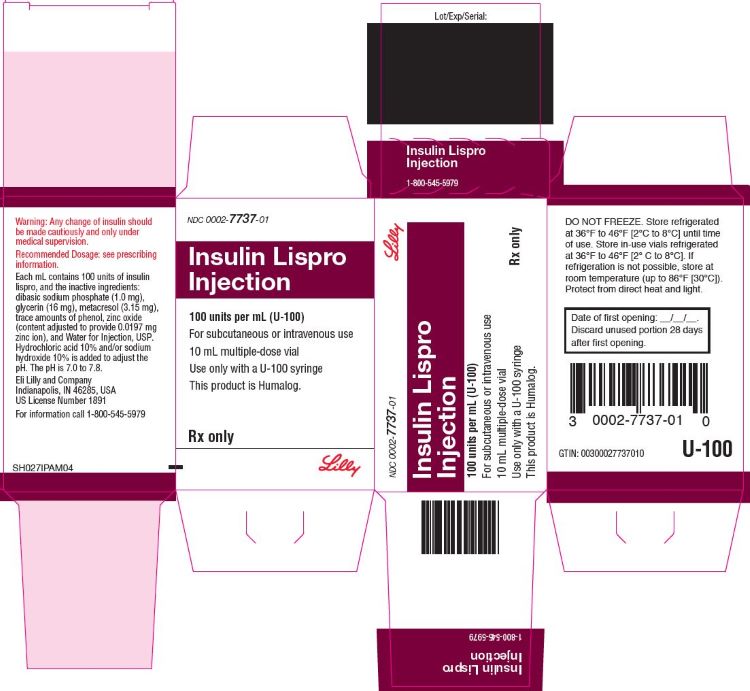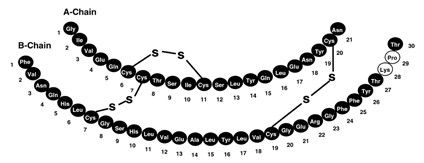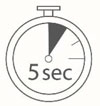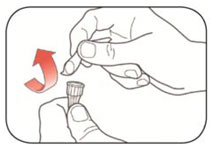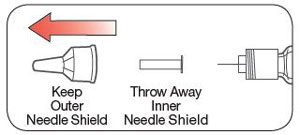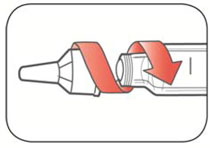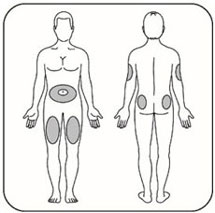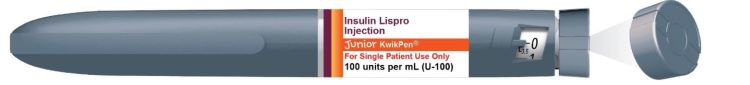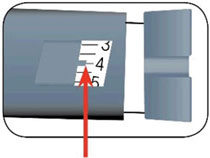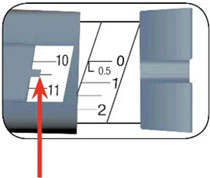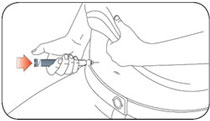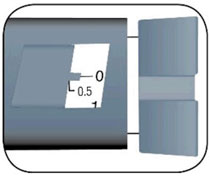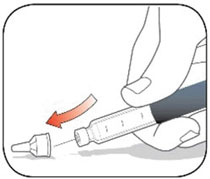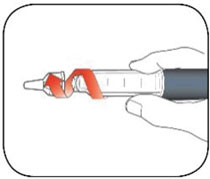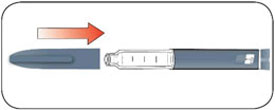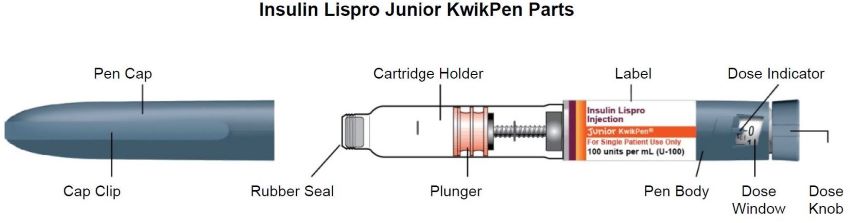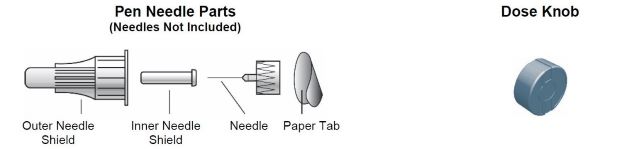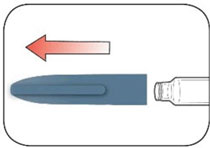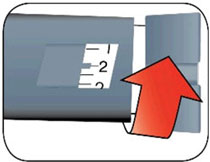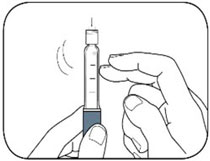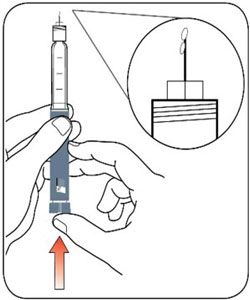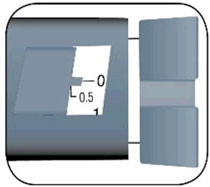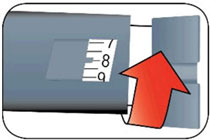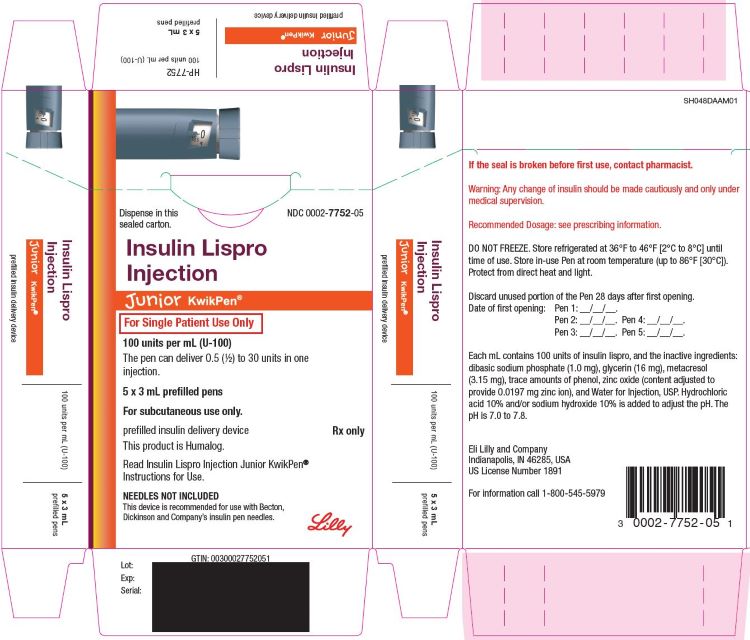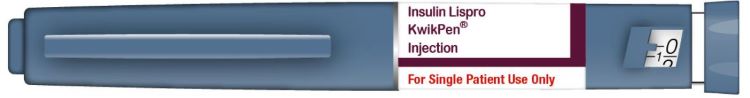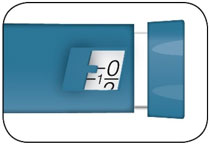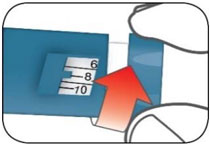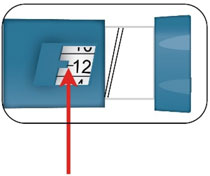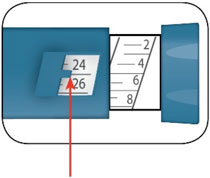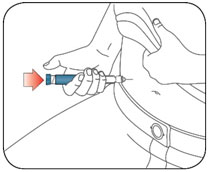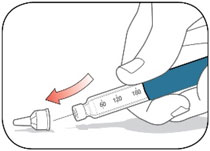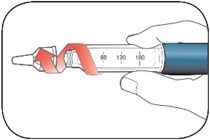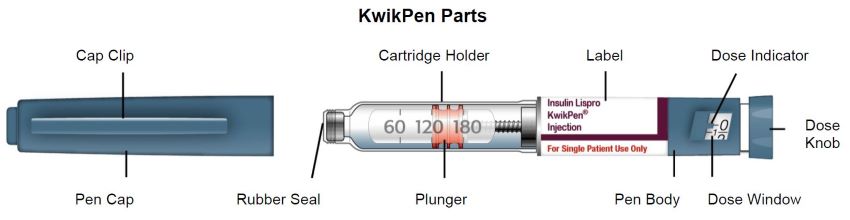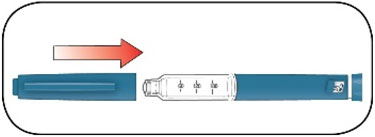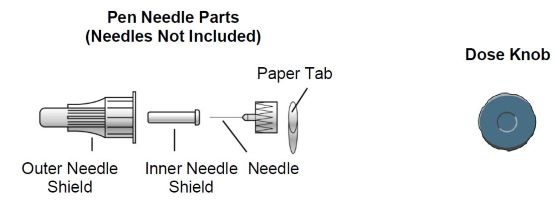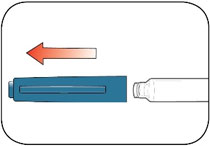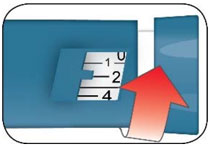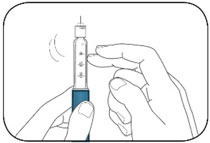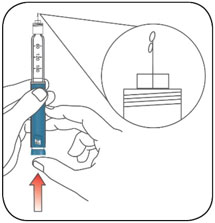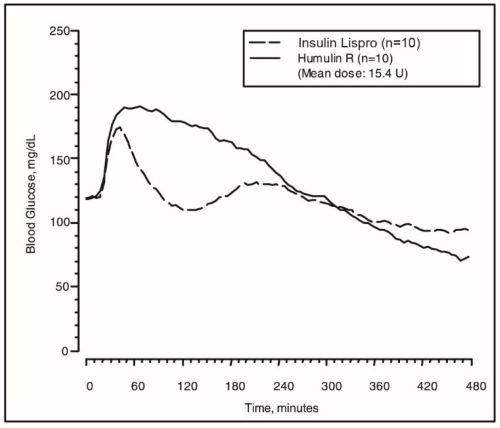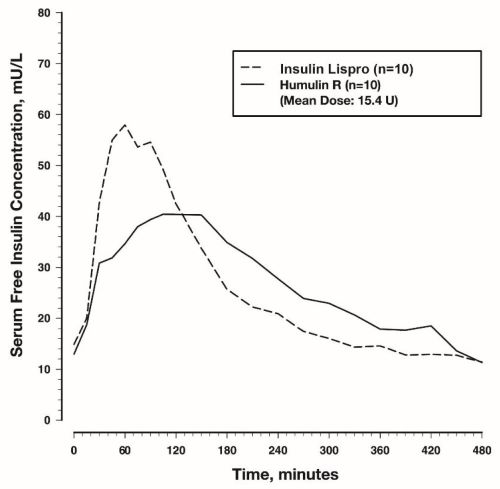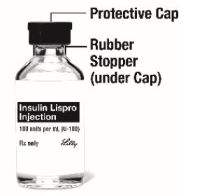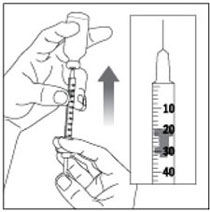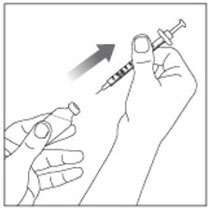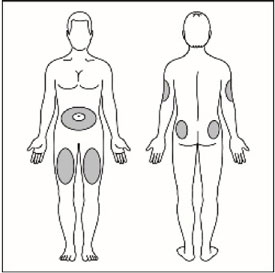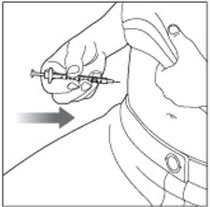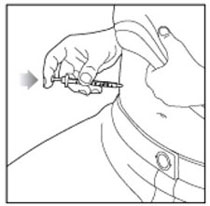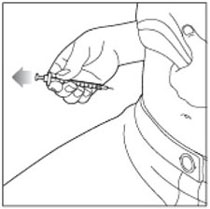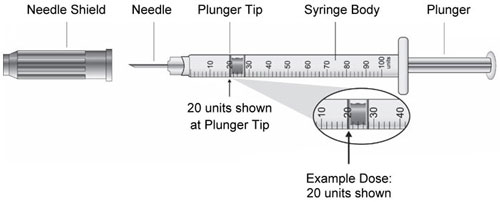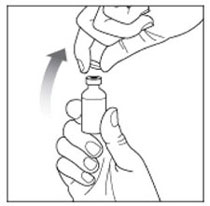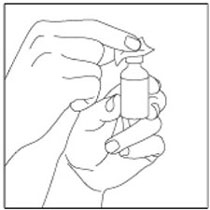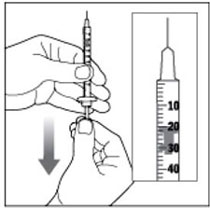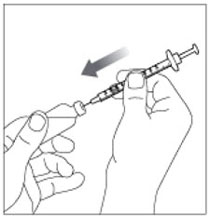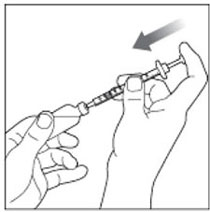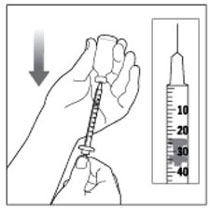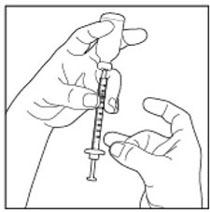 DRUG LABEL: Insulin Lispro
NDC: 0002-7737 | Form: INJECTION, SOLUTION
Manufacturer: Eli Lilly and Company
Category: prescription | Type: HUMAN PRESCRIPTION DRUG LABEL
Date: 20250617

ACTIVE INGREDIENTS: Insulin lispro 100 [iU]/1 mL
INACTIVE INGREDIENTS: Sodium Phosphate, Dibasic, Unspecified Form 1.0 mg/1 mL; Glycerin 16 mg/1 mL; Metacresol 3.15 mg/1 mL; Phenol; Zinc .0197 mg/1 mL; Water; Hydrochloric acid; Sodium hydroxide

HIGHLIGHTS OF PRESCRIBING INFORMATION

These highlights do not include all the information needed to use INSULIN LISPRO safely and effectively. See full prescribing information for INSULIN LISPRO.
INSULIN LISPRO injection, for subcutaneous or intravenous use
Initial U.S. Approval: 1996
This product is HUMALOG® (insulin lispro).

1 INDICATIONS AND USAGE

Insulin Lispro is a rapid acting human insulin analog indicated to improve glycemic control in adult and pediatric patients with diabetes mellitus. (1)

2 DOSAGE AND ADMINISTRATION

- See Full Prescribing Information for important administration instructions. (2.1, 2.2, 2.3, 2.4)
- Subcutaneous Injection (2.2):
  - Administer Insulin Lispro by subcutaneous injection into the abdominal wall, thigh, upper arm, or buttocks within 15 minutes before a meal or immediately after a meal.
  - Rotate injection sites to reduce risk of lipodystrophy and localized cutaneous amyloidosis.
- Continuous subcutaneous infusion (Insulin Pump) (2.2):
  - Refer to the insulin infusion pump user manual to see if Humalog can be used. Use in accordance with the insulin pump instructions for use.
  - Administer Insulin Lispro by continuous subcutaneous infusion using an insulin pump in a region recommended in the instructions from the pump manufacturer.
  - Rotate infusion sites to reduce risk of lipodystrophy and localized cutaneous amyloidosis.
- Intravenous Infusion (2.2):
  - Administer Insulin Lispro by intravenous infusion ONLY after dilution and under medical supervision.
- The dosage of Insulin Lispro must be individualized based on the route of administration and the individual's metabolic needs, blood glucose monitoring results and glycemic control goal. (2.3)
- Do not perform dose conversion when using the Insulin Lispro prefilled pens. The dose window shows the number of insulin units to be delivered and no conversion is needed. (2.1, 2.3)

3 DOSAGE FORMS AND STRENGTHS

Injection: 100 units/mL (U-100) is available as: (3)

- 10 mL multiple-dose vial
- 3 mL single-patient-use KwikPen® prefilled pen
- 3 mL single-patient-use Junior KwikPen® prefilled pen

4 CONTRAINDICATIONS

- Do not use during episodes of hypoglycemia. (4)
- Do not use in patients with hypersensitivity to Insulin Lispro or any of the excipients in Insulin Lispro. (4)

5 WARNINGS AND PRECAUTIONS

- Never share an Insulin Lispro prefilled pen or syringe between patients, even if the needle is changed. (5.1)
- Hyperglycemia or Hypoglycemia with Changes in Insulin Regimen: Make changes to a patient's insulin regimen (e.g., insulin strength, manufacturer, type, injection site or method of administration) under close medical supervision with increased frequency of blood glucose monitoring. (5.2)
- Hypoglycemia: May be life-threatening. Monitor blood glucose and increase monitoring frequency with changes to insulin dosage, use of glucose lowering medications, meal pattern, physical activity; in patients with renal or hepatic impairment; and in patients with hypoglycemia unawareness. (5.3, 7, 8.6, 8.7)
- Hypoglycemia Due to Medication Errors: Accidental mix-ups between insulin products can occur. Instruct patients to check insulin labels before injection. (5.4)
- Hypersensitivity Reactions: May be life-threatening. Discontinue Insulin Lispro, monitor and treat if indicated. (5.5)
- Hypokalemia: May be life-threatening. Monitor potassium levels in patients at risk of hypokalemia and treat if indicated. (5.6)
- Fluid Retention and Heart Failure with Concomitant Use of Thiazolidinediones (TZDs): Observe for signs and symptoms of heart failure; consider dosage reduction or discontinuation if heart failure occurs. (5.7)
- Hyperglycemia and Ketoacidosis Due to Insulin Pump Device Malfunction: Monitor glucose and administer Insulin Lispro by subcutaneous injection if pump malfunction occurs. (5.8)

6 ADVERSE REACTIONS

Adverse reactions associated with Insulin Lispro include hypoglycemia, allergic reactions, injection site reactions, lipodystrophy, pruritus, and rash. (6.1)

To report SUSPECTED ADVERSE REACTIONS, contact Eli Lilly and Company at 1-800-LillyRx (1-800-545-5979) or FDA at 1-800-FDA-1088 or www.fda.gov/medwatch.

7 DRUG INTERACTIONS

- Drugs that may increase the risk of hypoglycemia: antidiabetic agents, ACE inhibitors, angiotensin II receptor blocking agents, disopyramide, fibrates, fluoxetine, monoamine oxidase inhibitors, pentoxifylline, pramlintide, salicylates, somatostatin analog (e.g., octreotide), and sulfonamide antibiotics (7).
- Drugs that may decrease the blood glucose lowering effect: atypical antipsychotics, corticosteroids, danazol, diuretics, estrogens, glucagon, isoniazid, niacin, oral contraceptives, phenothiazines, progestogens (e.g., in oral contraceptives), protease inhibitors, somatropin, sympathomimetic agents (e.g., albuterol, epinephrine, terbutaline), and thyroid hormones (7).
- Drugs that may increase or decrease the blood glucose lowering effect: alcohol, beta-blockers, clonidine, lithium salts, and pentamidine (7).
- Drugs that may blunt the signs and symptoms of hypoglycemia: beta-blockers, clonidine, guanethidine, and reserpine (7).

FULL PRESCRIBING INFORMATION

1 INDICATIONS AND USAGE

Insulin Lispro is indicated to improve glycemic control in adult and pediatric patients with diabetes mellitus.

2 DOSAGE AND ADMINISTRATION

2.1 Important Administration Instructions

- Always check insulin labels before administration. This product is HUMALOG (insulin lispro) [see Warnings and Precautions (5.4)].
- Inspect Insulin Lispro visually before use. It should appear clear and colorless. Do not use Insulin Lispro if particulate matter or coloration is seen.
- Use Insulin Lispro prefilled pens with caution in patients with visual impairment that may rely on audible clicks to dial their dose.
- Do NOT mix Insulin Lispro with other insulins when using a continuous subcutaneous infusion pump.
- Do NOT perform dose conversion when using any Insulin Lispro prefilled pens. The dose window shows the number of insulin units to be delivered and no conversion is needed.

2.2 Administration Instructions for the Approved Routes of Administration

Subcutaneous Injection

- Administer the dose of Insulin Lispro within fifteen minutes before a meal or immediately after a meal by injection into the subcutaneous tissue of the abdominal wall, thigh, upper arm, or buttocks.
- Rotate the injection site within the same region from one injection to the next (abdominal wall, thigh, upper arm, or buttocks) to reduce the risk of lipodystrophy and localized cutaneous amyloidosis. Do not inject into areas of lipodystrophy or localized cutaneous amyloidosis [see Warnings and Precautions (5.2) and Adverse Reactions (6)].
- During changes to a patient's insulin regimen, increase the frequency of blood glucose monitoring [see Warnings and Precautions (5.2)].
- Insulin Lispro administered by subcutaneous injection should generally be used in regimens with an intermediate- or long-acting insulin.
- The Insulin Lispro KwikPen dials in 1 unit increments and delivers a maximum dose of 60 units per injection.
- The Insulin Lispro Junior KwikPen dials in 0.5 unit increments and delivers a maximum dose of 30 units per injection.

Subcutaneous Injection: Diluted Insulin Lispro

- Insulin Lispro may be diluted with Sterile Diluent for Insulin Lispro for subcutaneous injection ONLY under medical supervision. Dilute one part Insulin Lispro to:
  - Nine parts diluent to yield a concentration one-tenth that of Insulin Lispro (equivalent to U-10).
  - One part diluent to yield a concentration one-half that of Insulin Lispro (equivalent to U-50).
- Diluted Insulin Lispro for subcutaneous injection may be stored for 28 days when refrigerated at 41°F (5°C) and for 14 days at room temperature up to 86°F (30°C).

Continuous Subcutaneous Infusion (Insulin Pump)

- This Insulin Lispro product can be used with continuous subcutaneous insulin infusion pumps labeled for use with Humalog (insulin lispro). Refer to the insulin pump user manual to see if Humalog can be used. Use Insulin Lispro in accordance with the insulin pump system's instructions for use.
- Administer Insulin Lispro by continuous subcutaneous infusion in a region recommended in the instructions from the pump manufacturer.
- Rotate infusion sites within the same region to reduce the risk of lipodystrophy and localized cutaneous amyloidosis. Do not inject into areas of lipodystrophy or localized cutaneous amyloidosis [see Warnings and Precautions (5.2) and Adverse Reactions (6)].
- Train patients using continuous subcutaneous insulin infusion therapy to administer insulin by injection and have alternate insulin therapy available in case of insulin pump failure [see Warnings and Precautions (5.8)].
- During changes to a patient's insulin regimen, increase the frequency of blood glucose monitoring [see Warnings and Precautions (5.2)].
- Change Insulin Lispro in the pump reservoir at least every 7 days or according to the pump user manual, whichever is shorter. Follow the Humalog-specific information for in-use time because Humalog-specific information may differ from general pump manual instructions.
- Change the infusion set and the infusion set insertion site according to the manufacturer's user manual.
- Do NOT dilute or mix Insulin Lispro when administering by continuous subcutaneous infusion.
- Do NOT expose Insulin Lispro in the pump reservoir to temperatures greater than 98.6°F (37°C).

Intravenous Administration

- Administer Insulin Lispro intravenously ONLY under medical supervision with close monitoring of blood glucose and potassium levels to avoid hypoglycemia and hypokalemia [see Warnings and Precautions (5.3, 5.6) and How Supplied/Storage and Handling (16.4)].
- Dilute Insulin Lispro to concentrations from 0.1 unit/mL to 1.0 unit/mL using 0.9% Sodium Chloride Injection, USP.
- Infusion bags prepared with Insulin Lispro are stable when stored in a refrigerator (2° to 8°C [36° to 46°F]) for 48 hours and then may be used at room temperature for up to an additional 48 hours.

2.3 Dosage Recommendations

- Individualize and adjust the dosage of Insulin Lispro based on route of administration, the individual's metabolic needs, blood glucose monitoring results and glycemic control goal.
- When switching from another insulin to Insulin Lispro. a different dosage of Insulin Lispro may be needed [see Warnings and Precautions (5.2)].
- Dosage modifications may be needed with changes in physical activity, changes in meal patterns (i.e., macronutrient content or timing of food intake), changes in renal or hepatic function or during acute illness [see Warnings and Precautions (5.2, 5.3) and Use in Specific Populations (8.6, 8.7)].
- Do NOT perform dose conversion when using the Insulin Lispro prefilled pens. The dose window shows the number of insulin units to be delivered and no conversion is needed.

2.4 Dosage Modifications for Drug Interactions

Dosage modification may be needed when Insulin Lispro is used concomitantly with certain drugs [see Drug Interactions (7)].

2.5 Instructions for Mixing with Other Insulins

The table below includes administration instructions regarding mixing Insulin Lispro with other insulins.

Insulin Lispro subcutaneous injection route | - Insulin Lispro may be mixed with NPH insulin preparations ONLY. - If Insulin Lispro is mixed with NPH insulin, Insulin Lispro should be drawn into the syringe first. Injection should occur immediately after mixing.
Insulin Lispro continuous subcutaneous infusion route (Insulin Pump) | Do NOT mix Insulin Lispro with any other insulin.

3 DOSAGE FORMS AND STRENGTHS

Injection: 100 units/mL (U-100) clear and colorless solution available as:

- 10 mL multiple-dose vial
- 3 mL single-patient-use KwikPen prefilled pen
- 3 mL single-patient-use Junior KwikPen prefilled pen

4 CONTRAINDICATIONS

Insulin Lispro is contraindicated:

- during episodes of hypoglycemia [see Warnings and Precautions (5.3)].
- in patients who are hypersensitive to Insulin Lispro or to any of the excipients in Insulin Lispro [see Warnings and Precautions (5.5)].

5 WARNINGS AND PRECAUTIONS

5.1 Never Share an Insulin Lispro Prefilled Pen or Syringe Between Patients

Insulin Lispro prefilled pens must never be shared between patients, even if the needle is changed. Patients using Insulin Lispro vials must never share needles or syringes with another person. Sharing poses a risk for transmission of blood-borne pathogens.

5.2 Hyperglycemia or Hypoglycemia with Changes in Insulin Regimen

Changes in an insulin regimen (e.g., insulin strength, manufacturer, type, injection site or method of administration) may affect glycemic control and predispose to hypoglycemia [see Warnings and Precautions (5.3)] or hyperglycemia. Repeated insulin injections into areas of lipodystrophy or localized cutaneous amyloidosis have been reported to result in hyperglycemia; and a sudden change in the injection site (to an unaffected area) has been reported to result in hypoglycemia [see Adverse Reactions (6)].

Make any changes to a patient's insulin regimen under close medical supervision with increased frequency of blood glucose monitoring. Advise patients who have repeatedly injected into areas of lipodystrophy or localized cutaneous amyloidosis to change the injection site to unaffected areas and closely monitor for hypoglycemia. For patients with type 2 diabetes, dosage adjustments of concomitant antidiabetic products may be needed.

5.3 Hypoglycemia

Hypoglycemia is the most common adverse reaction associated with insulins, including Insulin Lispro. Severe hypoglycemia can cause seizures, may be life-threatening, or cause death. Hypoglycemia can impair concentration ability and reaction time; this may place an individual and others at risk in situations where these abilities are important (e.g., driving or operating other machinery).

Hypoglycemia can happen suddenly, and symptoms may differ in each individual and change over time in the same individual. Symptomatic awareness of hypoglycemia may be less pronounced in patients with longstanding diabetes, in patients with diabetic nerve disease, in patients using medications that block the sympathetic nervous system (e.g., beta-blockers) [see Drug Interactions (7)], or in patients who experience recurrent hypoglycemia.

Risk Factors for Hypoglycemia

The risk of hypoglycemia after an injection is related to the duration of action of the insulin and, in general, is highest when the glucose lowering effect of the insulin is maximal. As with all insulins, the glucose lowering effect time course of Insulin Lispro may vary in different individuals or at different times in the same individual and depends on many conditions, including the area of injection as well as the injection site blood supply and temperature [see Clinical Pharmacology (12.2)]. Other factors which may increase the risk of hypoglycemia include changes in meal pattern (e.g., macronutrient content or timing of meals), changes in level of physical activity, or changes to co-administered medication [see Drug Interactions (7)]. Patients with renal or hepatic impairment may be at higher risk of hypoglycemia [see Use in Specific Populations (8.6, 8.7)].

Risk Mitigation Strategies for Hypoglycemia

Patients and caregivers must be educated to recognize and manage hypoglycemia. Self-monitoring of blood glucose plays an essential role in the prevention and management of hypoglycemia. In patients at higher risk for hypoglycemia and patients who have reduced symptomatic awareness of hypoglycemia, increased frequency of blood glucose monitoring is recommended.

5.4 Hypoglycemia Due to Medication Errors

Accidental mix-ups between insulin products have been reported. To avoid medication errors between Insulin Lispro and other insulins, instruct patients to always check the insulin label before each injection.

5.5 Hypersensitivity Reactions

Severe, life-threatening, generalized allergy, including anaphylaxis, can occur with insulins, including Insulin Lispro. If hypersensitivity reactions occur, discontinue Insulin Lispro; treat per standard of care and monitor until symptoms and signs resolve [see Adverse Reactions (6.1)]. Insulin Lispro is contraindicated in patients who have had hypersensitivity reactions to Insulin Lispro or any of the excipients in Insulin Lispro [see Contraindications (4)].

5.6 Hypokalemia

All insulins, including Insulin Lispro, cause a shift in potassium from the extracellular to intracellular space, possibly leading to hypokalemia. Untreated hypokalemia may cause respiratory paralysis, ventricular arrhythmia, and death. Monitor potassium levels in patients at risk for hypokalemia if indicated (e.g., patients using potassium-lowering medications, patients taking medications sensitive to serum potassium concentrations).

5.7 Fluid Retention and Heart Failure with Concomitant Use of PPAR-gamma Agonists

Thiazolidinediones (TZDs), which are peroxisome proliferator-activated receptor (PPAR)-gamma agonists, can cause dose-related fluid retention, particularly when used in combination with insulin. Fluid retention may lead to or exacerbate heart failure. Patients treated with insulin, including Insulin Lispro, and a PPAR-gamma agonist should be observed for signs and symptoms of heart failure. If heart failure develops, it should be managed according to current standards of care, and discontinuation or dose reduction of the PPAR-gamma agonist must be considered.

5.8 Hyperglycemia and Ketoacidosis Due to Insulin Pump Device Malfunction

Malfunction of the insulin pump or insulin infusion set or insulin degradation can rapidly lead to hyperglycemia and ketoacidosis. Prompt identification and correction of the cause of hyperglycemia or ketosis is necessary. Interim subcutaneous injections with Insulin Lispro may be required. Patients using continuous subcutaneous insulin infusion pump therapy must be trained to administer insulin by injection and have alternate insulin therapy available in case of pump failure [see How Supplied/Storage and Handling (16.2) and Patient Counseling Information (17)].

6 ADVERSE REACTIONS

The following adverse reactions are discussed elsewhere:

- Hypoglycemia [see Warnings and Precautions (5.3)].
- Hypoglycemia Due to Medication Errors [see Warnings and Precautions (5.4)].
- Hypersensitivity Reactions [see Warnings and Precautions (5.5)].
- Hypokalemia [see Warnings and Precautions (5.6)].

6.1 Clinical Trials Experience

Because clinical trials are conducted under widely varying designs, the adverse reaction rates reported in one clinical trial may not be easily compared with those rates reported in another clinical trial, and may not reflect the rates actually observed in clinical practice.

Common adverse reactions, excluding hypoglycemia, were defined as events that occurred in ≥5% of patients treated with Insulin Lispro or regular human insulin. The frequencies of adverse reactions during Insulin Lispro clinical trials in patients with type 1 diabetes mellitus and type 2 diabetes mellitus are listed in the tables below.

Table 1: Adverse Reactions That Occurred in ≥5% in Patients with Type 1 Diabetes Mellitus
 | Insulin Lispro (%) (n=81) | Regular human insulin (%) (n=86)
Flu syndrome | 34.6 | 32.6
Pharyngitis | 33.3 | 33.7
Rhinitis | 24.7 | 29.1
Headache | 29.6 | 22.1
Pain | 19.8 | 16.3
Cough increased | 17.3 | 17.4
Infection | 13.6 | 20.9
Nausea | 6.2 | 15.1
Accidental injury | 8.6 | 11.6
Surgical procedure | 6.2 | 14.0
Fever | 6.2 | 11.6
Abdominal pain | 7.4 | 8.1
Asthenia | 7.4 | 8.1
Bronchitis | 7.4 | 7.0
Diarrhea | 8.6 | 5.8
Dysmenorrhea | 6.2 | 7.0
Myalgia | 7.4 | 5.8
Urinary tract infection | 6.2 | 4.7

Table 2: Adverse Reactions That Occurred in ≥5% in Patients with Type 2 Diabetes Mellitus
 | Insulin Lispro (%) (n=714) | Regular human insulin (%) (n=709)
Headache | 11.6 | 9.3
Pain | 10.8 | 10.0
Infection | 10.1 | 7.6
Pharyngitis | 6.6 | 8.2
Rhinitis | 8.1 | 6.6
Flu syndrome | 6.2 | 8.2
Surgical procedure | 7.4 | 6.8

Insulin initiation and intensification of glucose control

Intensification or rapid improvement in glucose control has been associated with a transitory, reversible ophthalmologic refraction disorder, worsening of diabetic retinopathy, and acute painful peripheral neuropathy. However, long-term glycemic control decreases the risk of diabetic retinopathy and neuropathy.

Hypoglycemia

Hypoglycemia is the most commonly observed adverse reaction in patients using insulin, including Insulin Lispro.

Lipodystrophy

Long-term use of insulin, including Insulin Lispro, can cause lipodystrophy at the site of repeated insulin injections or infusion. Lipodystrophy includes lipohypertrophy (thickening of adipose tissue) and lipoatrophy (thinning of adipose tissue), and may affect insulin absorption [see Dosage and Administration (2.2)].

Weight gain

Weight gain can occur with insulins, including Insulin Lispro, and has been attributed to the anabolic effects of insulin and the decrease in glucosuria.

Peripheral Edema

Insulins, including Insulin Lispro, may cause sodium retention and edema, particularly if previously poor metabolic control is improved by intensified insulin therapy.

Adverse Reactions with Continuous Subcutaneous Insulin Infusion (CSII)

In a 12-week, randomized, crossover study in adult patients with type 1 diabetes (n=39), the rates of catheter occlusions and infusion site reactions were similar for Insulin Lispro and regular human insulin treated patients (see Table 3).

Table 3: Catheter Occlusions and Infusion Site Reactions
 | Insulin Lispro (n=38) | Regular human insulin (n=39)
Catheter occlusions/month | 0.09 | 0.10
Infusion site reactions | 2.6% (1/38) | 2.6% (1/39)

In a randomized, 16-week, open-label, parallel design study of pediatric patients with type 1 diabetes, adverse reactions related to infusion-site reactions were similar for Insulin Lispro and insulin aspart (21% of 100 patients versus 17% of 198 patients, respectively). In both groups, the most frequently reported infusion site reactions were infusion site erythema and infusion site reaction.

Allergic Reactions

Local Allergy — As with any insulin, patients taking Insulin Lispro may experience redness, swelling, or itching at the site of the injection. These minor reactions usually resolve in a few days to a few weeks, but in some occasions, may require discontinuation of Insulin Lispro.

Systemic Allergy — Severe, life-threatening, generalized allergy, including anaphylaxis, may occur with any insulin, including Insulin Lispro. Generalized allergy to insulin may cause whole body rash (including pruritus), dyspnea, wheezing, hypotension, tachycardia, or diaphoresis.

In controlled clinical trials, pruritus (with or without rash) was seen in 17 patients receiving regular human insulin (n=2969) and 30 patients receiving Insulin Lispro (n=2944).

Localized reactions and generalized myalgias have been reported with injected metacresol, which is an excipient in Insulin Lispro [see Contraindications (4)].

Antibody Production

In large clinical trials with patients with type 1 (n=509) and type 2 (n=262) diabetes mellitus, anti-insulin antibody (insulin lispro-specific antibodies, insulin-specific antibodies, cross-reactive antibodies) formation was evaluated in patients receiving both regular human insulin and Insulin Lispro (including patients previously treated with human insulin and naive patients). As expected, the largest increase in the antibody levels occurred in patients new to insulin therapy. The antibody levels peaked by 12 months and declined over the remaining years of the study. These antibodies do not appear to cause deterioration in glycemic control or necessitate an increase in insulin dose. There was no statistically significant relationship between the change in the total daily insulin dose and the change in percent antibody binding for any of the antibody types.

6.2 Postmarketing Experience

The following additional adverse reactions have been identified during post-approval use of Insulin Lispro. Because these reactions are reported voluntarily from a population of uncertain size, it is not always possible to reliably estimate their frequency or establish a causal relationship to drug exposure.

Medication errors in which other insulins have been accidentally substituted for Insulin Lispro have been identified during post-approval use.

Localized cutaneous amyloidosis at the injection site has occurred. Hyperglycemia has been reported with repeated insulin injections into areas of localized cutaneous amyloidosis; hypoglycemia has been reported with a sudden change to an unaffected injection site.

7 DRUG INTERACTIONS

The table below includes clinically significant drug interactions with Insulin Lispro.

Drugs That May Increase the Risk of Hypoglycemia
Drugs: | Antidiabetic agents, ACE inhibitors, angiotensin II receptor blocking agents, disopyramide, fibrates, fluoxetine, monoamine oxidase inhibitors, pentoxifylline, pramlintide, salicylates, somatostatin analog (e.g., octreotide), and sulfonamide antibiotics.
Intervention: | Dose adjustment and increased frequency of glucose monitoring may be required when Insulin Lispro is co-administered with these drugs.
Drugs That May Decrease the Blood Glucose Lowering Effect of Insulin Lispro
Drugs: | Atypical antipsychotics (e.g., olanzapine and clozapine), corticosteroids, danazol, diuretics, estrogens, glucagon, isoniazid, niacin, oral contraceptives, phenothiazines, progestogens (e.g., in oral contraceptives), protease inhibitors, somatropin, sympathomimetic agents (e.g., albuterol, epinephrine, terbutaline), and thyroid hormones.
Intervention: | Dose adjustment and increased frequency of glucose monitoring may be required when Insulin Lispro is co-administered with these drugs.
Drugs That May Increase or Decrease the Blood Glucose Lowering Effect of Insulin Lispro
Drugs: | Alcohol, beta-blockers, clonidine, and lithium salts. Pentamidine may cause hypoglycemia, which may sometimes be followed by hyperglycemia.
Intervention: | Dose adjustment and increased frequency of glucose monitoring may be required when Insulin Lispro is co-administered with these drugs.
Drugs That May Blunt Signs and Symptoms of Hypoglycemia
Drugs: | Beta-blockers, clonidine, guanethidine and reserpine
Intervention: | Increased frequency of glucose monitoring may be required when Insulin Lispro is co-administered with these drugs.

8 USE IN SPECIFIC POPULATIONS

8.1 Pregnancy

Risk Summary

Published studies with insulin lispro used during pregnancy have not reported an association between insulin lispro and the induction of major birth defects, miscarriage, or adverse maternal or fetal outcomes (see Data). There are risks to the mother and fetus associated with poorly controlled diabetes in pregnancy (see Clinical Considerations).

Pregnant rats and rabbits were exposed to insulin lispro in animal reproduction studies during organogenesis. No adverse effects on embryo/fetal viability or morphology were observed in offspring of rats exposed to insulin lispro at a dose approximately 3 times the human subcutaneous dose of 1 unit insulin lispro/kg/day. No adverse effects on embryo/fetal development were observed in offspring of rabbits exposed to insulin lispro at doses up to approximately 0.2 times the human subcutaneous dose of 1 unit/kg/day (see Data).

The estimated background risk of major birth defects is 6-10% in women with pre-gestational diabetes with a HbA1c >7 and has been reported to be as high as 20-25% in women with a HbA1c >10. The estimated background risk of miscarriage for the indicated population is unknown. In the U.S. general population, the estimated background risk of major birth defects and miscarriage in clinically recognized pregnancies is 2-4% and 15-20%, respectively.

Clinical Considerations

Disease-associated maternal and/or embryo/fetal risk

Poorly controlled diabetes in pregnancy increases the maternal risk for diabetic ketoacidosis, pre-eclampsia, spontaneous abortions, preterm delivery, and delivery complications. Poorly controlled diabetes increases the fetal risk for major birth defects, stillbirth, and macrosomia related morbidity.

Data

Human Data

Published data from retrospective studies and meta-analyses do not report an association with insulin lispro and major birth defects, miscarriage, or adverse maternal or fetal outcomes when insulin lispro is used during pregnancy. However, these studies cannot definitely establish or exclude the absence of any risk because of methodological limitations including small sample size, selection bias, confounding by unmeasured factors, and some lacking comparator groups.

Animal Data

In a combined fertility and embryo-fetal development study, female rats were given subcutaneous insulin lispro injections of 1, 5, and 20 units/kg/day (0.2, 0.8, and 3 times the human subcutaneous dose of 1 unit insulin lispro/kg/day, based on units/body surface area, respectively) from 2 weeks prior to cohabitation through Gestation Day 19. There were no adverse effects on female fertility, implantation, or fetal viability and morphology. However, fetal growth retardation was produced at the 20 units/kg/day-dose as indicated by decreased fetal weight and an increased incidence of fetal runts/litter.

In an embryo-fetal development study in pregnant rabbits, insulin lispro doses of 0.1, 0.25, and 0.75 unit/kg/day (0.03, 0.08, and 0.2 times the human subcutaneous dose of 1 unit insulin lispro/kg/day, based on units/body surface area, respectively) were injected subcutaneously on Gestation days 7 through 19. There were no adverse effects on fetal viability, weight, and morphology at any dose.

8.2 Lactation

Risk Summary

Available data from published literature suggests that exogenous human insulin products, including insulin lispro, are transferred into human milk. There are no adverse reactions reported in breastfed infants in the literature. There are no data on the effects of exogenous human insulin products, including insulin lispro, on milk production. The developmental and health benefits of breastfeeding should be considered along with the mother's clinical need for insulin, any potential adverse effects on the breastfed child from Insulin Lispro or from the underlying maternal condition.

8.4 Pediatric Use

The safety and effectiveness of Insulin Lispro to improve glycemic control have been established in pediatric patients with diabetes mellitus. Use of Insulin Lispro for this indication is supported by evidence from adequate and well-controlled studies in 831 pediatric patients with type 1 diabetes mellitus aged 3 years and older and from studies in adults with diabetes mellitus [see Adverse Reactions (6.1), Clinical Pharmacology (12.3), and Clinical Studies (14)].

8.5 Geriatric Use

Of the total number of patients (n=2,834) in eight clinical studies of Insulin Lispro, twelve percent (n=338) were 65 years of age or over. The majority of these patients had type 2 diabetes. HbA1c values and hypoglycemia rates did not differ by age. Pharmacokinetic/pharmacodynamic studies to assess the effect of age on the onset of Insulin Lispro action have not been performed.

8.6 Renal Impairment

Patients with renal impairment may be at increased risk of hypoglycemia and may require more frequent Insulin Lispro dose adjustment and more frequent blood glucose monitoring [see Clinical Pharmacology (12.3)].

8.7 Hepatic Impairment

Patients with hepatic impairment may be at increased risk of hypoglycemia and may require more frequent Insulin Lispro dose adjustment and more frequent blood glucose monitoring [see Clinical Pharmacology (12.3)].

10 OVERDOSAGE

Excess insulin administration may cause hypoglycemia and hypokalemia. Mild episodes of hypoglycemia usually can be treated with oral glucose. Adjustments in drug dosage, meal patterns, or exercise may be needed. More severe episodes with coma, seizure, or neurologic impairment may be treated with a glucagon product for emergency use or concentrated intravenous glucose. Sustained carbohydrate intake and observation may be necessary because hypoglycemia may recur after apparent clinical recovery. Hypokalemia must be corrected appropriately.

11 DESCRIPTION

Insulin lispro is a rapid-acting human insulin analog produced by recombinant DNA technology utilizing a non-pathogenic laboratory strain of Escherichia coli. Insulin lispro differs from human insulin in that the amino acid proline at position B28 is replaced by lysine and the lysine in position B29 is replaced by proline. Chemically, it is Lys(B28), Pro(B29) human insulin analog and has the empirical formula C257H383N65O77S6 and a molecular weight of 5.808 kDa, both identical to that of human insulin.

Insulin lispro has the following primary structure:

Insulin Lispro injection is a sterile, clear, and colorless solution for subcutaneous or intravenous use.

Each mL of Insulin Lispro contains 100 units of insulin lispro, and the inactive ingredients: dibasic sodium phosphate (1.0 mg), glycerin (16 mg), metacresol (3.15 mg), trace amounts of phenol, zinc oxide (content adjusted to provide 0.0197 mg zinc ion), and Water for Injection, USP.

Insulin Lispro has a pH of 7.0 to 7.8.

Hydrochloric acid 10% and/or sodium hydroxide 10% is added to adjust the pH.

12 CLINICAL PHARMACOLOGY

12.1 Mechanism of Action

Regulation of glucose metabolism is the primary activity of insulins and insulin analogs, including insulin lispro. Insulins lower blood glucose by stimulating peripheral glucose uptake by skeletal muscle and fat, and by inhibiting hepatic glucose production. Insulins inhibit lipolysis and proteolysis, and enhance protein synthesis.

12.2 Pharmacodynamics

Insulin Lispro has been shown to be equipotent to human insulin on a molar basis. One unit of Insulin Lispro has the same glucose-lowering effect as one unit of regular human insulin. Studies in normal volunteers and patients with diabetes demonstrated that Insulin Lispro has a more rapid onset of action and a shorter duration of activity than regular human insulin when given subcutaneously.

The time course of action of insulin and insulin analogs, such as Insulin Lispro, may vary considerably in different individuals or within the same individual. The parameters of Insulin Lispro activity (time of onset, peak time, and duration) as designated in Figure 1 should be considered only as general guidelines. The rate of insulin absorption, and consequently the onset of activity are known to be affected by the site of injection, exercise, and other variables [see Warnings and Precautions (5.2)].

Figure 1: Blood Glucose Levels After Subcutaneous Injection of Regular Human Insulin or Insulin Lispro (0.2 unit/kg) Immediately Before a High Carbohydrate Meal in 10 Patients with Type 1 Diabetesa.

a Baseline insulin concentration was maintained by infusion of 0.2 mU/min/kg human insulin.

Intravenous Administration — The glucose lowering effect of intravenously administered Insulin Lispro was tested in 21 patients with type 1 diabetes. For the study, the patients' usual doses of insulin were held and blood glucose concentrations were allowed to reach a stable range of 200 to 260 mg/dL during a one to three hours run-in phase. The run-in phase was followed by a 6-hour assessment phase. During the assessment phase, patients received intravenous Insulin Lispro at an initial infusion rate of 0.5 units/hour. The infusion rate of Insulin Lispro could be adjusted at regular timed intervals to achieve and maintain blood glucose concentrations between 100 to 160 mg/dL.

The mean blood glucose levels during the assessment phase for patients on Insulin Lispro therapy are summarized below in Table 4. All patients achieved the targeted glucose range at some point during the 6-hour assessment phase. At the endpoint, blood glucose was within the target range (100 to 160 mg/dL) for 17 of 20 patients treated with Insulin Lispro. The average time (±SE) required to attain near normoglycemia was 129 ± 14 minutes for Insulin Lispro.

Table 4: Mean Blood Glucose Concentrations (mg/dL) During Intravenous Infusions of Insulin Lispro
Time from Start of Infusion (minutes) | Mean Blood Glucose (mg/dL) Intravenous
0 | 224 ± 16
30 | 205 ± 21
60 | 195 ± 20
120 | 165 ± 26
180 | 140 ± 26
240 | 123 ± 20
300 | 120 ± 27
360 | 122 ± 25
a Results shown as mean ± SD

12.3 Pharmacokinetics

Absorption and Bioavailability — Studies in healthy volunteers and patients with diabetes demonstrated that Insulin Lispro is absorbed more quickly than regular human insulin. In healthy volunteers given subcutaneous doses of Insulin Lispro ranging from 0.1 to 0.4 unit/kg, peak serum levels were seen 30 to 90 minutes after dosing. When healthy volunteers received equivalent doses of regular human insulin, peak insulin levels occurred between 50 to 120 minutes after dosing. Similar results were seen in patients with type 1 diabetes (see Figure 2).

Figure 2: Serum Insulin Lispro and Insulin Levels After Subcutaneous Injection of Regular Human Insulin or Insulin Lispro (0.2 unit/kg) Immediately Before a High Carbohydrate Meal in 10 Patients with Type 1 Diabetesa.

a Baseline insulin concentration was maintained by infusion of 0.2 mU/min/kg human insulin.

Insulin Lispro was absorbed at a consistently faster rate than regular human insulin in healthy male volunteers given 0.2 unit/kg at abdominal, deltoid, or femoral subcutaneous sites. After Insulin Lispro was administered in the abdomen, serum drug levels were higher and the duration of action was slightly shorter than after deltoid or thigh administration. Bioavailability of Insulin Lispro is similar to that of regular human insulin. The absolute bioavailability after subcutaneous injection ranges from 55% to 77% with doses between 0.1 to 0.2 unit/kg, inclusive.

Distribution — When administered intravenously as bolus injections of 0.1 and 0.2 U/kg dose in two separate groups of healthy subjects, the mean volume of distribution of Insulin Lispro appeared to decrease with increase in dose (1.55 and 0.72 L/kg, respectively) in contrast to that of regular human insulin for which, the volume of distribution was comparable across the two dose groups (1.37 and 1.12 L/kg for 0.1 and 0.2 U/kg dose, respectively).

Metabolism — Human metabolism studies have not been conducted. However, animal studies indicate that the metabolism of Insulin Lispro is identical to that of regular human insulin.

Elimination — After subcutaneous administration of Insulin Lispro, the t1/2 is shorter than that of regular human insulin (1 versus 1.5 hours, respectively). When administered intravenously, Insulin Lispro and regular human insulin demonstrated similar dose-dependent clearance, with a mean clearance of 21.0 mL/min/kg and 21.4 mL/min/kg, respectively (0.1 unit/kg dose), and 9.6 mL/min/kg and 9.4 mL/min/kg, respectively (0.2 unit/kg dose). Accordingly, Insulin Lispro demonstrated a mean t1/2 of 0.85 hours (51 minutes) and 0.92 hours (55 minutes), respectively for 0.1 unit/kg and 0.2 unit/kg doses, and regular human insulin mean t1/2 was 0.79 hours (47 minutes) and 1.28 hours (77 minutes), respectively for 0.1 unit/kg and 0.2 unit/kg doses.

Specific Populations

The effects of age, gender, race, obesity, pregnancy, or smoking on the pharmacokinetics of Insulin Lispro have not been studied.

Renal Impairment — Type 2 diabetic patients with varying degree of renal impairment showed no difference in pharmacokinetics of regular insulin and Insulin Lispro. However, the sensitivity of the patients to insulin did change, with an increased response to insulin as the renal function declined. Some studies with human insulin have shown increased circulating levels of insulin in patients with renal impairment [see Use in Specific Populations (8.6)].

Hepatic Impairment — Type 2 diabetic patients with impaired hepatic function showed no effect on the pharmacokinetics of Insulin Lispro as compared to patients with no hepatic dysfunction. However, some studies with human insulin have shown increased circulating levels of insulin in patients with liver failure [see Use in Specific Populations (8.7)].

13 NONCLINICAL TOXICOLOGY

13.1 Carcinogenesis, Mutagenesis, Impairment of Fertility

Standard 2-year carcinogenicity studies in animals have not been performed. In Fischer 344 rats, a 12-month repeat-dose toxicity study was conducted with insulin lispro at subcutaneous doses of 20 and 200 units/kg/day (approximately 3 and 32 times the human subcutaneous dose of 1 unit/kg/day, based on units/body surface area). Insulin lispro did not produce important target organ toxicity including mammary tumors at any dose.

Insulin lispro was not mutagenic in the following genetic toxicity assays: bacterial mutation, unscheduled DNA synthesis, mouse lymphoma, chromosomal aberration and micronucleus assays.

Male fertility was not compromised when male rats given subcutaneous insulin lispro injections of 5 and 20 units/kg/day (0.8 and 3 times the human subcutaneous dose of 1 unit/kg/day, based on units/body surface area) for 6 months were mated with untreated female rats. In a combined fertility, perinatal, and postnatal study in male and female rats given 1, 5, and 20 units/kg/day subcutaneously (0.2, 0.8, and 3 times the human subcutaneous dose of 1 unit/kg/day, based on units/body surface area), mating and fertility were not adversely affected in either gender at any dose.

13.2 Animal Toxicology and/or Pharmacology

In standard biological assays in fasted rabbits, 0.2 unit/kg of insulin lispro injected subcutaneously had the same glucose-lowering effect and had a more rapid onset of action as 0.2 unit/kg of regular human insulin.

14 CLINICAL STUDIES

The safety and efficacy of Insulin Lispro were studied in pediatric and adult patients with type 1 diabetes (n=789) and adult patients with type 2 diabetes (n=722).

14.1 Type 1 Diabetes – Adults and Pediatric Patients Aged 12 Years and Older

A 12-month, randomized, parallel, open-label, active-controlled study was conducted in patients with type 1 diabetes to assess the safety and efficacy of Insulin Lispro (n=81) compared with Humulin® R [insulin human injection (100 units/mL)] (n=86). Insulin Lispro was administered by subcutaneous injection immediately prior to meals and Humulin R was administered 30 to 45 minutes before meals. Humulin® U [ULTRALENTE® human insulin (rDNA origin) extended zinc suspension] was administered once or twice daily as the basal insulin. There was a 2- to 4-week run-in period with Humulin R and Humulin U before randomization. Most patients were Caucasian (97%). Forty-seven percent of the patients were male. The mean age was 31 years (range 12 to 70 years). Glycemic control, the total daily doses of Insulin Lispro and Humulin R, and the incidence of severe hypoglycemia (as determined by the number of events that were not self-treated) were similar in the two treatment groups. There were no episodes of diabetic ketoacidosis in either treatment group.

Table 5: Type 1 Diabetes Mellitus – Adults and Pediatric Patients Aged 12 years and Older
Treatment Duration Treatment in Combination with: | 12 months Humulin U
 | Insulin Lispro | Humulin R
N | 81 | 86
Baseline HbA1c (%)a | 8.2 ± 1.4 | 8.3 ± 1.7
Change from baseline HbA1c (%)a | -0.1 ± 0.9 | 0.1 ± 1.1
Treatment Difference in HbA1c Mean (95% confidence interval) | 0.4 (0.0, 0.8)
Baseline short-acting insulin dose (units/kg/day) | 0.3 ± 0.1 | 0.3 ± 0.1
End-of-Study short-acting insulin dose (units/kg/day) | 0.3 ± 0.1 | 0.3 ± 0.1
Change from baseline short-acting insulin dose (units/kg/day) | 0.0 ± 0.1 | 0.0 ± 0.1
Baseline Body weight (kg) | 72 ± 12.7 | 71 ± 11.3
Weight change from baseline (kg) | 1.4 ± 3.6 | 1.0 ± 2.6
Patients with severe hypoglycemia (n, %)b | 14 (17%) | 18 (21%)
a Values are Mean ± SD
b Severe hypoglycemia refers to hypoglycemia for which patients were not able to self-treat.

14.2 Type 1 Diabetes – Pediatric Patients

An 8-month, crossover study of pediatric patients with type 1 diabetes (n=463), aged 9 to 19 years, compared two subcutaneous multiple-dose treatment regimens: Insulin Lispro or Humulin R, both administered with Humulin N (NPH human insulin) as the basal insulin. Insulin Lispro achieved glycemic control comparable to Humulin R, as measured by HbA1c (see Table 6), and both treatment groups had a comparable incidence of hypoglycemia. In a 9-month, crossover study of pediatric patients (n=60) with type 1 diabetes, aged 3 to 11 years, Insulin Lispro administered immediately before meals, Insulin Lispro administered immediately after meals and Humulin R administered 30 minutes before meals resulted in similar glycemic control, as measured by HbA1c, and incidence of hypoglycemia, regardless of treatment group.

Table 6: Pediatric Subcutaneous Administration of Insulin Lispro in Type 1 Diabetes
 |  | End point
 | Baseline | Insulin Lispro + NPH | Humulin R + NPH
HbA1c (%)a | 8.6 ± 1.5 | 8.7 ± 1.5 | 8.7 ± 1.6
Change from baseline HbA1c (%)a | — | 0.1 ± 1.1 | 0.1 ± 1.3
Short-acting insulin dose (units/kg/day)a | 0.5 ± 0.2 | 0.5 ± 0.2 | 0.5 ± 0.2
Change from baseline short-acting insulin dose (units/kg/day)a | — | 0.01 ± 0.1 | -0.01 ± 0.1
Body weight (kg)a | 59.1 ± 13.1 | 61.1 ± 12.7 | 61.4 ± 12.9
Weight change from baseline (kg)a | — | 2.0 ± 3.1 | 2.3 ± 3.0
Patients with severe hypoglycemia (n, %)b | — | 5 (1.1%) | 5 (1.1%)
Diabetic ketoacidosis (n, %) | — | 11 (2.4%) | 9 (1.9%)
a Values are Mean ± SD
b Severe hypoglycemia refers to hypoglycemia that required glucagon or glucose injection or resulted in coma.

14.3 Type 1 Diabetes – Adults: Continuous Subcutaneous Insulin Infusion

To evaluate the administration of Insulin Lispro via external insulin pumps, two open-label, crossover design studies were performed in patients with type 1 diabetes. One study involved 39 patients, ages 19 to 58 years, treated for 24 weeks with Insulin Lispro or regular human insulin. After 12 weeks of treatment, the mean HbA1c values decreased from 7.8% to 7.2% in the Insulin Lispro -treated patients and from 7.8% to 7.5% in the regular human insulin-treated patients. Another study involved 60 patients (mean age 39, range 15 to 58 years) treated for 24 weeks with either Insulin Lispro or buffered regular human insulin. After 12 weeks of treatment, the mean HbA1c values decreased from 7.7% to 7.4% in the Insulin Lispro-treated patients and remained unchanged from 7.7% in the buffered regular human insulin-treated patients. Rates of hypoglycemia were comparable between treatment groups in both studies.

14.4 Type 1 Diabetes – Pediatric Patients: Continuous Subcutaneous Insulin Infusion

A randomized, 16-week, open-label, parallel design, study of pediatric patients with type 1 diabetes (n=298) aged 4 to 18 years compared two subcutaneous infusion regimens administered via an external insulin pump: insulin aspart (n=198) or Insulin Lispro (n=100). These two treatments resulted in comparable changes from baseline in HbA1c and comparable rates of hypoglycemia after 16 weeks of treatment (see Table 7). Infusion site reactions were similar between groups.

Table 7: Pediatric Insulin Pump Study in Type 1 Diabetes (16 weeks; n=298)
 | Insulin Lispro | Aspart
N | 100 | 198
Baseline HbA1c (%)a | 8.2 ± 0.8 | 8.0 ± 0.9
Change from Baseline HbA1c (%) | -0.1 ± 0.7 | -0.1 ± 0.8
Treatment Difference in HbA1c, Mean (95% confidence interval) | 0.1 (-0.3, 0.1)
Baseline insulin dose (units/kg/24 hours)a | 0.9 ± 0.3 | 0.9 ± 0.3
End-of-Study insulin dose (units/kg/24 hours)a | 0.9 ± 0.2 | 0.9 ± 0.2
Patients with severe hypoglycemia (n, %)b | 8 (8%) | 19 (10%)
Diabetic ketoacidosis (n, %) | 0 (0) | 1 (0.5%)
Baseline body weight (kg)a | 55.5 ± 19.0 | 54.1 ± 19.7
Weight Change from baseline (kg)a | 1.6 ± 2.1 | 1.8 ± 2.1
a Values are Mean ± SD
b Severe hypoglycemia refers to hypoglycemia associated with central nervous system symptoms and requiring the intervention of another person or hospitalization.

14.5 Type 2 Diabetes – Adults

A 6-month randomized, crossover, open-label, active-controlled study was conducted in insulin-treated patients with type 2 diabetes (n=722) to assess the safety and efficacy of Insulin Lispro for 3 months followed by Humulin R for 3 months or the reverse sequence. Insulin Lispro was administered by subcutaneous injection immediately before meals and Humulin R was administered 30 to 45 minutes before meals. Humulin® N [NPH human insulin (rDNA origin) isophane suspension] or Humulin U was administered once or twice daily as the basal insulin. All patients participated in a 2- to 4-week run-in period with Humulin R and Humulin N or Humulin U. Most of the patients were Caucasian (88%), and the numbers of men and women in each group were approximately equal. The mean age was 58.6 years (range 23.8 to 85 years). The average body mass index (BMI) was 28.2 kg/m^2. During the study, the majority of patients used Humulin N (84%) compared with Humulin U (16%) as their basal insulin. The reductions from baseline in HbA1c and the incidence of severe hypoglycemia (as determined by the number of events that were not self-treated) were similar between the two treatments from the combined groups (see Table 8).

Table 8: Type 2 Diabetes Mellitus — Adults
 |  | End point
 | Baseline | Insulin Lispro + Basal | Humulin R + Basal
HbA1c (%)a | 8.9 ± 1.7 | 8.2 ± 1.3 | 8.2 ± 1.4
Change from baseline HbA1c (%)a | — | -0.7 ± 1.4 | -0.7 ± 1.3
Short-acting insulin dose (units/kg/day)a | 0.3 ± 0.2 | 0.3 ± 0.2 | 0.3 ± 0.2
Change from baseline short-acting insulin dose (units/kg/day)a | — | 0.0 ± 0.1 | 0.0 ± 0.1
Body weight (kg)a | 80 ± 15 | 81 ± 15 | 81 ± 15
Weight change from baseline | — | 0.8 ± 2.7 | 0.9 ± 2.6
Patients with severe hypoglycemia (n, %)b | — | 15 (2%) | 16 (2%)
a Values are Mean ± SD
b Severe hypoglycemia refers to hypoglycemia for which patients were not able to self-treat.

16 HOW SUPPLIED/STORAGE AND HANDLING

16.1 How Supplied

Insulin Lispro injection is a clear and colorless solution available as:

Insulin Lispro | Total Volume | Concentration | NDC Number | Package Size
U-100 multiple-dose vial | 10 mL | 100 units/mL | 0002-7737-01 | 1 vial
U-100 single-patient-use KwikPen | 3 mL | 100 units/mL | 0002-8222-59 | 5 pens
U-100 single-patient-use Junior KwikPen | 3 mL | 100 units/mL | 0002-7752-05 | 5 pens

The KwikPen dials in 1-unit increments. The Junior KwikPen dials in 0.5-unit increments.

Each Insulin Lispro prefilled pen is for single-patient-use only. Insulin Lispro prefilled pens must never be shared between patients, even if the needle is changed. Patients using Insulin Lispro vials must never share needles or syringes with another person.

16.2 Storage and Handling

Dispense in the original sealed carton with the enclosed Instructions for Use.

Protect from direct heat and light. Do not freeze and do not use if it has been frozen.

See table below for storage information:

 | Not In-Use (Unopened) Room Temperature (Up to 86°F [30°C]) | Not In-Use (Unopened) Refrigerated (36° to 46°F [2° to 8°C]) | In-Use (Opened) (see temperature below*)
10 mL multiple-dose vial | 28 days | Until expiration date | 28 days Refrigerated or room temperature.
3 mL single-patient-use Insulin Lispro KwikPen | 28 days | Until expiration date | 28 days Room temperature only (Do not refrigerate)
3 mL single-patient-use Insulin Lispro Junior KwikPen | 28 days | Until expiration date | 28 days Room temperature only (Do not refrigerate)
* When stored at room temperature, Insulin Lispro can only be used for a total of 28 days, including both not in-use (unopened) and in-use (opened) storage time.

Use in an External Insulin Pump — Change the Insulin Lispro in the reservoir at least every 7 days, or according to the pump user manual, whichever is shorter, or after exposure to temperatures that exceed 98.6°F (37°C).

Storage of Diluted Insulin Lispro for Subcutaneous Injection — Diluted Insulin Lispro for subcutaneous injection may be stored for 28 days when refrigerated at 41°F (5°C) and 14 days at room temperature up to 86°F (30°C) [see Dosage and Administration (2.2)]. Do not dilute Insulin Lispro used in an external insulin pump.

Storage of Intravenous Infusion Preparations with Insulin Lispro

Intravenous infusion bags prepared with Insulin Lispro maybe stored for 48 hours when refrigerated at 36° to 46°F (2° to 8°C). The prepared intravenous bags may then be used at room temperature for up to an additional 48 hours [see Dosage and Administration (2.2)].

17 PATIENT COUNSELING INFORMATION

Advise the patient to read the FDA-approved patient labeling (Patient Information and Instructions for Use).

Never Share an Insulin Lispro Prefilled Pen or Syringe Between Patients

Advise patients that they must never share an Insulin Lispro prefilled pen with another person, even if the needle is changed. Advise patients using Insulin Lispro vials not to share needles or syringes with another person. Sharing poses a risk for transmission of blood-borne pathogens [see Warnings and Precautions (5.1)].

Hyperglycemia or Hypoglycemia

Instruct patients on self-management procedures including glucose monitoring, proper injection technique, and management of hypoglycemia and hyperglycemia, especially at initiation of Insulin Lispro therapy. Instruct patients on handling of special situations such as intercurrent conditions (illness, stress, or emotional disturbances), an inadequate or skipped insulin dose, inadvertent administration of an increased insulin dose, inadequate food intake, and skipped meals. Instruct patients on the management of hypoglycemia.

Inform patients that their ability to concentrate and react may be impaired as a result of hypoglycemia. Advise patients who have frequent hypoglycemia or reduced or absent warning signs of hypoglycemia to use caution when driving or operating machinery [see Warnings and Precautions (5.3)].

Advise patients that changes in insulin regimen can predispose to hyperglycemia or hypoglycemia and that changes in insulin regimen should be made under close medical supervision [see Warnings and Precautions (5.2)].

Hypoglycemia due to Medication Errors

Instruct patients to always check the insulin container label before each injection to avoid mix-ups between insulin products [see Warnings and Precautions (5.4)].

Hypersensitivity Reactions

Advise patients that hypersensitivity reactions have occurred with Insulin Lispro. Inform patients on the symptoms of hypersensitivity reactions [see Warnings and Precautions (5.5)].

Instructions For Patients Using Continuous Subcutaneous Insulin Pumps

- Train patients in intensive insulin therapy with multiple injections and in the function of their pump and pump accessories.
- Instruct patients to follow healthcare provider recommendations when setting pump basal rates and bolus settings.
- This Insulin Lispro product can be used with continuous subcutaneous insulin infusion pumps labeled for use with Humalog (insulin lispro) – refer to the insulin pump user manual to see if Humalog can be used. See recommended reservoir and infusion sets in the insulin pump user manual.
- Instruct patients to replace insulin in the reservoir at least every 7 days, or according to the pump user manual, whichever is shorter; infusion sets and infusion set insertion sites should be changed in accordance with the manufacturers' user manual. By following this schedule, patients avoid insulin degradation, infusion set occlusion, and loss of the insulin preservative.
- Instruct patients to discard insulin exposed to temperatures higher than 98.6°F (37°C). The temperature of the insulin may exceed ambient temperature when the pump housing, cover, tubing or sport case is exposed to sunlight or radiant heat.
- Instruct patients to inform healthcare provider and select a new site for infusion if infusion site becomes erythematous, pruritic, or thickened.
- Instruct patients on the risk of rapid hyperglycemia and ketosis due to pump malfunction, infusion set occlusion, leakage, disconnection or kinking, and degraded insulin. Instruct patients on the risk of hypoglycemia from pump malfunction. If these problems cannot be promptly corrected, instruct patients to resume therapy with subcutaneous insulin injection and contact their healthcare provider [see Warnings and Precautions (5) and How Supplied/Storage and Handling (16.2)].

Manufactured by:
Eli Lilly and Company
Indianapolis, IN 46285, USA
US License Number 1891

Humalog® and KwikPen® are registered trademarks of Eli Lilly and Company.

Copyright © 1996, 2023, Eli Lilly and Company. All rights reserved.

LIS-0008-USPI-20230921

Patient Package Insert

PATIENT INFORMATION
Insulin Lispro [IHN-soo-lihn LIYS-proh]
injection, for subcutaneous or intravenous use
100 units per mL
This product is HUMALOG® (insulin lispro).

Do not share your Insulin Lispro prefilled pens or syringes with other people, even if the needle has been changed. You may give other people a serious infection or get a serious infection from them.

What is Insulin Lispro?

- Insulin Lispro is a man-made fast-acting insulin used to control high blood sugar in adults and children with diabetes mellitus.

Who should not take Insulin Lispro?
Do not take Insulin Lispro if you:

- are having an episode of low blood sugar (hypoglycemia).
- have an allergy to Insulin Lispro or any of the ingredients in Insulin Lispro. See the end of this Patient Information leaflet for a complete list of ingredients in Insulin Lispro.

What should I tell my healthcare provider before taking Insulin Lispro?
Before taking Insulin Lispro, tell your healthcare provider about all of your medical conditions, including if you:

- have kidney or liver problems.
- take any other medicines, especially ones called TZDs (thiazolidinediones).
- have heart failure or other heart problems. If you have heart failure, it may get worse while you take TZDs with Insulin Lispro.
- are pregnant or plan to become pregnant. Talk with your healthcare provider about the best way to control your blood sugar if you plan to become pregnant or while you are pregnant.
- are breastfeeding or plan to breastfeed. Talk with your healthcare provider about the best way to feed your baby while taking Insulin Lispro.

Tell your healthcare provider about all the medicines you take, including prescription and over-the-counter medicines, vitamins, and herbal supplements.
Before you start taking Insulin Lispro, talk to your healthcare provider about low blood sugar and how to manage it.

How should I take Insulin Lispro?

- Read the Instructions for Use that comes with your Insulin Lispro.
- Take Insulin Lispro exactly as your healthcare provider tells you to. Your healthcare provider should tell you how much Insulin Lispro to take and when to take it.
- Insulin Lispro starts acting fast. Inject Insulin Lispro within 15 minutes before or right after you eat a meal.
- Know the type, strength and amount of insulin you take. Do not change the type or amount of insulin you take unless your healthcare provider tells you to. The amount of insulin and the best time for you to take your insulin may need to change if you take different types of insulin.
- Check your insulin label each time you give your injection to make sure you are taking the correct insulin.
- Inject Insulin Lispro under the skin (subcutaneously) of your stomach area, buttocks, upper legs or upper arms, or by continuous infusion under the skin (subcutaneously) through an insulin pump into an area of your body recommended in the instructions that come with your insulin pump.
- Change (rotate) your injection sites within the area you choose with each dose to reduce your risk of getting lipodystrophy (pits in skin or thickened skin) and localized cutaneous amyloidosis (skin with lumps) at the injection sites.
  - Do not use the exact same spot for each injection.
  - Do not inject where the skin has pits, is thickened, or has lumps.
  - Do not inject where the skin is tender, bruised, scaly or hard, or into scars or damaged skin.
- Always use a new needle for each injection to help prevent infections and blocked needles. Do not reuse or share your needles with other people. You may give other people a serious infection or get a serious infection from them.
- Check your blood sugar levels. Ask your healthcare provider what your blood sugars should be and when you should check your blood sugar levels.

Keep Insulin Lispro and all medicines out of the reach of children.

Your dose of Insulin Lispro may need to change because of a:

- change in physical activity or exercise, weight gain or loss, increased stress, illness, change in diet, or because of other medicines you take.

What should I avoid while taking Insulin Lispro?
While taking Insulin Lispro do not:

- drive or operate heavy machinery, until you know how Insulin Lispro affects you.
- drink alcohol or take prescription or over-the-counter medicines that contain alcohol.

What are the possible side effects of Insulin Lispro?
Insulin Lispro may cause serious side effects that can lead to death, including:

- low blood sugar (hypoglycemia). Signs and symptoms of low blood sugar may include:

- dizziness or light-headedness
- sweating
- confusion
- headache
- blurred vision

- slurred speech
- shakiness
- fast heartbeat
- anxiety, irritability or mood changes
- hunger

Your healthcare provider may prescribe a glucagon product for emergency use so that someone else can give you glucagon if your blood sugar becomes too low (severe hypoglycemia) and you are unable to take sugar by mouth.

- serious allergic reactions (whole body allergic reaction). Get medical help right away, if you have any of these signs or symptoms of a severe allergic reaction:

- a rash over your whole body
- trouble breathing
- a fast heartbeat

- sweating
- feel faint

- low potassium in your blood (hypokalemia).
- heart failure. Taking certain diabetes pills called thiazolidinediones or “TZDs” with Insulin Lispro may cause heart failure in some people. This can happen even if you have never had heart failure or heart problems before. If you already have heart failure it may get worse while you take TZDs with Insulin Lispro. Your healthcare provider should monitor you closely while you are taking TZDs with Insulin Lispro. Tell your healthcare provider if you have any new or worse symptoms of heart failure including:

- shortness of breath
- swelling of your ankles or feet

- sudden weight gain

Treatment with TZDs and Insulin Lispro may need to be adjusted or stopped by your healthcare provider if you have new or worse heart failure.
Get emergency medical help if you have:

- trouble breathing
- shortness of breath
- fast heartbeat
- swelling of your face, tongue, or throat

- sweating
- extreme drowsiness
- dizziness
- confusion

The most common side effects of Insulin Lispro include:

- low blood sugar (hypoglycemia)
- reactions at your injection site
- skin thickening or pits at the injection site
  (lipodystrophy)

- weight gain
- swelling in your hands or feet
- itching
- rash

These are not all the possible side effects of Insulin Lispro. Call your doctor for medical advice about side effects. You may report side effects to FDA at 1-800-FDA-1088.

General information about the safe and effective use of Insulin Lispro.
Medicines are sometimes prescribed for purposes other than those listed in a Patient Information leaflet. Do not take Insulin Lispro for a condition for which it was not prescribed. Do not give Insulin Lispro to other people, even if they have the same symptoms that you have. It may harm them.
This Patient Information leaflet summarizes the most important information about Insulin Lispro. If you would like more information, talk with your healthcare provider. You can ask your pharmacist or healthcare provider for information about Insulin Lispro that is written for health professionals.

What are the ingredients in Insulin Lispro?
Active ingredient: insulin lispro
Inactive ingredients: dibasic sodium phosphate, glycerin, hydrochloric acid, metacresol, trace amounts of phenol, sodium hydroxide, zinc oxide (zinc ion), and Water for Injection, USP.
Humalog® is a registered trademark of Eli Lilly and Company.
Manufactured by: Eli Lilly and Company, Indianapolis, IN 46285, USA, US License Number 1891
Copyright © 1996, 2023, Eli Lilly and Company. All rights reserved.
For more information, call 1-800-545-5979.

This Patient Information has been approved by the U.S. Food and Drug Administration

Revised: 07/2023

LIS-0007-PPI-20230721

Vial Instructions for Use

INSTRUCTIONS FOR USE

Insulin Lispro [IHN-soo-lihn LIYS-proh]

injection, for subcutaneous use

10 mL multiple-dose vial (100 units per mL, U-100)

This product is HUMALOG® (insulin lispro).

Read this Instructions for Use before you start taking Insulin Lispro and each time you get a new vial. There may be new information. This information does not take the place of talking to your healthcare provider about your medical condition or your treatment.

Do not share your needles or syringes with other people, even if the needle has been changed. You may give other people a serious infection or get a serious infection from them.

Supplies needed to give your injection

- a multiple-dose Insulin Lispro vial
- a U-100 insulin syringe and needle
- 2 alcohol swabs
- gauze
- 1 sharps container for throwing away used needles and syringes. See “Disposing of used needles and syringes” at the end of these instructions.

Vial

Syringe

Preparing your Insulin Lispro dose

- Wash your hands with soap and water.
- Check the Insulin Lispro label to make sure you are taking the right type of insulin. This is especially important if you use more than 1 type of insulin.
- Insulin Lispro should look clear and colorless. Do not use Insulin Lispro if it is thick, cloudy, or colored, or if you see lumps or particles in it.
- Do not use Insulin Lispro past the expiration date printed on the label or 28 days after you first use it.
- Always use a new syringe and needle for each injection to prevent infections and blocked needles. Do not reuse or share your syringes or needles with other people. You may give other people a serious infection or get a serious infection from them.

Step 1:
If you are using a new vial, pull off the plastic Protective Cap, but do not remove the Rubber Stopper.

Step 2:
Wipe the Rubber Stopper with an alcohol swab.

Step 3:
Remove the Needle Shield from the syringe by pulling the Needle Shield straight off. Hold the syringe with the needle pointing up. Pull down on the Plunger until the Plunger Tip reaches the line for the number of units for your prescribed dose.

(Example Dose: 20 units shown)

Step 4:
Push the needle through the Rubber Stopper of the vial.

Step 5:
Push the Plunger all the way in. This puts air into the vial.

Step 6:
Turn the vial and syringe upside down and slowly pull the Plunger down until the Plunger Tip is a few units past the line for your prescribed dose.

(Example Dose: 20 units Plunger is shown at 24 units)

If there are air bubbles, tap the syringe gently a few times to let any air bubbles rise to the top.

Step 7:
Slowly push the Plunger up until the Plunger Tip reaches the line for your prescribed dose.
Check the syringe to make sure that you have the right dose.

(Example Dose: 20 units shown)

Step 8:
Pull the syringe out of the Rubber Stopper of the vial.

If you use Insulin Lispro with NPH insulin:

- NPH insulin is the only type of insulin that can be mixed with Insulin Lispro. Do not mix Insulin Lispro with any other type of insulin.
- Insulin Lispro should be drawn up into the syringe first, before you draw up your NPH insulin. Talk to your healthcare provider if you are not sure about the right way to mix Insulin Lispro and NPH insulin.
- Give your injection right away.

Giving your Insulin Lispro with a syringe

- Inject your insulin exactly as your healthcare provider has shown you. Your healthcare provider should tell you if you should pinch the skin before injecting.
- Insulin Lispro starts acting fast, so give your injection within 15 minutes before or right after you eat a meal.
- Change (rotate) your injection sites within the area you choose for each dose to reduce your risk of getting lipodystrophy (pits in skin or thickened skin) and localized cutaneous amyloidosis (skin with lumps) at the injection sites.
- Do not inject where the skin has pits, is thickened, or has lumps.
- Do not inject where the skin is tender, bruised, scaly or hard, or into scars or damaged skin.

Step 9:
Choose your injection site.
Insulin Lispro is injected under the skin (subcutaneously) of your stomach area (abdomen), buttocks, upper legs or upper arms.
Wipe the skin with an alcohol swab. Let the injection site dry before you inject your dose.

Step 10:
Insert the needle into your skin.

Step 11:
Push down on the Plunger to inject your dose.
The needle should stay in your skin for at least 5 seconds to make sure you have injected all of your insulin dose.

Step 12:
Pull the needle out of your skin.

- If you see blood after you take the needle out of your skin, press the injection site with a piece of gauze or an alcohol swab. Do not rub the area.
- Do not recap the needle. Recapping the needle can lead to a needle stick injury.

Giving your Insulin Lispro using an insulin pump

- Insulin Lispro should be given into an area of your body recommended in the instructions that come with your insulin pump.
- Change your infusion set and rotate the infusion set insertion site according to the manufacturer's user manual.
- Change (rotate) your insertion sites within the area you choose for each insertion to reduce your risk of getting lipodystrophy (pits in skin or thickened skin) and localized cutaneous amyloidosis (skin with lumps) at the insertion sites. Do not insert into the exact same spot for each insertion. Do not insert where the skin has pits, is thickened, or has lumps. Do not insert where the skin is tender, bruised, scaly or hard, or into scars or damaged skin.
- This Insulin Lispro product can be used with the continuous subcutaneous insulin infusion pumps labeled for use with Humalog (insulin lispro) – refer to the insulin pump user manual to see if Humalog can be used.
- Change the insulin in the reservoir at least every 7 days or according to the pump user manual, whichever is shorter, even if you have not used all of the insulin.
- Do not dilute or mix Insulin Lispro with any other type of insulin in your insulin pump.
- See your insulin pump manual for instructions or talk to your healthcare provider.

Disposing of used needles and syringes

- Put your used needles and syringes in a FDA-cleared sharps disposal container right away after use. Do not throw away (dispose of) loose needles and syringes in your household trash.
- If you do not have a FDA-cleared sharps disposal container, you may use a household container that is:
  - made of a heavy-duty plastic,
  - can be closed with a tight-fitting, puncture-resistant lid, without sharps being able to come out,
  - upright and stable during use,
  - leak-resistant, and
  - properly labeled to warn of hazardous waste inside the container.
- When your sharps disposal container is almost full, you will need to follow your community guidelines for the right way to dispose of your sharps disposal container. There may be state or local laws about how you should throw away used needles and syringes. For more information about safe sharps disposal, and for specific information about sharps disposal in the state that you live in, go to the FDA's website at: http://www.fda.gov/safesharpsdisposal.
- Do not dispose of your used sharps disposal container in your household trash unless your community guidelines permit this. Do not recycle your used sharps disposal container.

How should I store Insulin Lispro?

All unopened vials:

- Store all unopened vials in the refrigerator at 36°F to 46°F (2°C to 8°C).
- Do not freeze. Do not use if Insulin Lispro has been frozen.
- Keep away from heat and out of direct light.
- Unopened vials can be used until the expiration date on the carton and label, if they have been stored in the refrigerator.
- Unopened vials should be thrown away after 28 days, if they are stored at room temperature.

After vials have been opened:

- Store opened vials in the refrigerator or at room temperature up to 86°F (30°C) for up to 28 days.
- Keep vials away from heat and out of direct light.
- Throw away all opened vials after 28 days of use, even if there is insulin left in the vial.

Insulin Lispro in an insulin pump:

- Throw away Insulin Lispro in the pump reservoir if it has been exposed to temperatures higher than 98.6°F (37°C).

Keep Insulin Lispro vials, syringes, needles and all medicines out of the reach of children.

If you have any questions or problems with your Insulin Lispro, contact Lilly at 1-800-Lilly-Rx (1-800-545-5979) or call your healthcare provider for help.

Manufactured by:
Eli Lilly and Company
Indianapolis, IN 46285, USA
US License Number 1891

This Instructions for Use has been approved by the U.S. Food and Drug Administration.

Humalog® is a registered trademark of Eli Lilly and Company.

Instructions for Use revised: July/2023

Copyright © 1996, 2023, Eli Lilly and Company. All rights reserved.

LISVL-0006-IFU-20230721

KwikPen (U-100) Instructions for Use

INSTRUCTIONS FOR USE

Insulin Lispro [IHN-soo-lihn LIYS-proh]

KwikPen®

injection, for subcutaneous use

3 mL single-patient-use pen (100 units per mL)

This product is HUMALOG® (insulin lispro).

Read the Instructions for Use before you start taking Insulin Lispro and each time you get another KwikPen®. There may be new information. This information does not take the place of talking to your healthcare provider about your medical condition or your treatment.

Do not share your Insulin Lispro KwikPen with other people, even if the needle has been changed. You may give other people a serious infection or get a serious infection from them.

Insulin Lispro KwikPen (“Pen”) is a disposable single-patient-use prefilled pen containing 300 units of insulin lispro. You can give yourself more than 1 dose from the Pen. Each turn (click) of the Dose Knob dials 1 unit of insulin. You can give from 1 to 60 units in a single injection. If your dose is more than 60 units, you will need to give yourself more than 1 injection. The Plunger only moves a little with each injection, and you may not notice that it moves. The Plunger will only reach the end of the cartridge when you have used all 300 units in the Pen.

People who are blind or have vision problems should not use the Pen without help from a person trained to use the Pen.

How to recognize your Insulin Lispro KwikPen

- Pen color: Dark blue
- Dose Knob: Dark blue
- Labels: White label with burgundy stripe

Supplies you will need to give your injection

- Insulin Lispro KwikPen
- KwikPen compatible Needle (Becton, Dickinson and Company Pen Needles recommended)
- Alcohol swab
- Gauze

Preparing your Pen

- Wash your hands with soap and water.
- Check your Pen to make sure you are taking the right type of insulin. This is especially important if you use more than 1 type of insulin.
- Do not use your Pen past the expiration date printed on the Label or for more than 28 days after you first start using the Pen.
- Always use a new needle for each injection to help prevent infections and blocked needles. Do not reuse or share your needles with other people. You may give other people a serious infection or get a serious infection from them.

Step 1:

- Pull the Pen Cap straight off.
  - Do not remove the Pen Label.
- Wipe the Rubber Seal with an alcohol swab.

Step 2:

- Check the liquid in the Pen.
  Insulin Lispro should look clear and colorless. Do not use if it is cloudy, colored, or has particles or clumps in it.

Step 3:

- Select a new Needle.
- Pull off the Paper Tab from the Outer Needle Shield.

Step 4:

- Push the capped Needle straight onto the Pen and twist the Needle on until it is tight.

Step 5:

- Pull off the Outer Needle Shield. Do not throw it away.
- Pull off the Inner Needle Shield and throw it away.

Priming your Pen

Prime before each injection.

- Priming your Pen means removing the air from the Needle and Cartridge that may collect during normal use and ensures that the Pen is working correctly.
- If you do not prime before each injection, you may get too much or too little insulin.

Step 6:

- To prime your Pen, turn the Dose Knob to select 2 units.

Step 7:

- Hold your Pen with the Needle pointing up. Tap the Cartridge Holder gently to collect air bubbles at the top.

Step 8:

- Continue holding your Pen with Needle pointing up. Push the Dose Knob in until it stops, and “0” is seen in the Dose Window. Hold the Dose Knob in and count to 5 slowly.
  You should see insulin at the tip of the Needle.
  - If you do not see insulin, repeat priming steps 6 to 8, no more than 4 times.
  - If you still do not see insulin, change the Needle and repeat priming steps 6 to 8.

Small air bubbles are normal and will not affect your dose.

Selecting your dose

- You can give from 1 to 60 units in a single injection.
- If your dose is more than 60 units, you will need to give more than 1 injection.
  - If you need help with dividing up your dose the right way, ask your healthcare provider.
  - Use a new Needle for each injection and repeat the priming step.

Step 9:

- Turn the Dose Knob to select the number of units you need to inject. The Dose Indicator should line up with your dose.
  - The Pen dials 1 unit at a time.
  - The Dose Knob clicks as you turn it.
  - Do not dial your dose by counting the clicks. You may dial the wrong dose. This may lead to you getting too much insulin or not enough insulin.
  - The dose can be corrected by turning the Dose Knob in either direction until the correct dose lines up with the Dose Indicator.
  - The even numbers (for example, 12) are printed on the dial.
  - The odd numbers, (for example, 25) after the number 1, are shown as full lines.
- Always check the number in the Dose Window to make sure you have dialed the correct dose.

(Example: 12 units shown in the Dose Window)
(Example: 25 units shown in the Dose Window)

- The Pen will not let you dial more than the number of units left in the Pen.
- If you need to inject more than the number of units left in the Pen, you may either:
  - inject the amount left in your Pen and then use a new Pen to give the rest of your dose, or
  - get a new Pen and inject the full dose.
- It is normal to see a small amount of insulin left in the Pen that you can not inject.

Giving your injection

- Inject your insulin as your healthcare provider has shown you.
- Change (rotate) your injection sites within the area you choose for each dose to reduce your risk of getting lipodystrophy (pits in skin or thickened skin) and localized cutaneous amyloidosis (skin with lumps) at the injection sites.
- Do not inject where the skin has pits, is thickened, or has lumps.
- Do not inject where the skin is tender, bruised, scaly or hard, or into scars or damaged skin.
- Do not try to change your dose while injecting.

Step 10:

- Choose your injection site.
  Insulin Lispro is injected under the skin (subcutaneously) of your stomach area, buttocks, upper legs or upper arms.
- Wipe your skin with an alcohol swab, and let your skin dry before you inject your dose.

Step 11:

- Insert the Needle into your skin.
- Push the Dose Knob all the way in.
- Continue to hold the Dose Knob in and slowly count to 5 before removing the Needle.
  Do not try to inject your insulin by turning the Dose Knob. You will not receive your insulin by turning the Dose Knob.

Step 12:

- Pull the Needle out of your skin.
  A drop of insulin at the Needle tip is normal. It will not affect your dose.
- Check the number in the Dose Window.
  - If you see “0” in the Dose Window, you have received the full amount you dialed.
  - If you do not see “0” in the Dose Window, do not redial. Insert the Needle into your skin and finish your injection.
  - If you still do not think you received the full amount you dialed for your injection, do not start over or repeat the injection. Monitor your blood glucose as instructed by your healthcare provider.
  - If you normally need to give 2 injections for your full dose, be sure to give your second injection.

The Plunger only moves a little with each injection, and you may not notice that it moves.
If you see blood after you take the Needle out of your skin, press the injection site lightly with a piece of gauze or an alcohol swab. Do not rub the area.

After your injection

Step 13:

- Carefully replace the Outer Needle Shield.

Step 14:

- Unscrew the capped Needle and throw it away (see Disposing of Pens and Needles section).
- Do not store the Pen with the Needle attached to prevent leaking, blocking the Needle, and air from entering the Pen.

Step 15:

- Replace the Pen Cap by lining up the Cap Clip with the Dose Indicator and pushing straight on.

Disposing of Pens and Needles

- The used Pen may be discarded in your household trash after you have removed the needle.
- Put your used needles in a FDA-cleared sharps disposal container right away after use. Do not throw away (dispose of) loose needles in your household trash.
- If you do not have a FDA-cleared sharps disposal container, you may use a household container that is:
  - made of a heavy-duty plastic,
  - can be closed with a tight-fitting, puncture-resistant lid, without sharps being able to come out,
  - upright and stable during use,
  - leak-resistant, and
  - properly labeled to warn of hazardous waste inside the container.
- When your sharps disposal container is almost full, you will need to follow your community guidelines for the right way to dispose of your sharps disposal container. There may be state or local laws about how you should throw away used needles and syringes. For more information about safe sharps disposal, and for specific information about sharps disposal in the state that you live in, go to the FDA's website at: http://www.fda.gov/safesharpsdisposal
- Do not dispose of your used sharps disposal container in your household trash unless your community guidelines permit this. Do not recycle your used sharps disposal container.

Storing your Pen

Unused Pens

- Store unused Pens in the refrigerator at 36°F to 46°F (2°C to 8°C).
- Do not freeze your insulin. Do not use if it has been frozen.
- Unused Pens may be used until the expiration date printed on the Label, if the Pen has been kept in the refrigerator.

In-use Pen

- Store the Pen you are currently using at room temperature [up to 86°F (30°C)]. Keep away from heat and light.
- Throw away the Insulin Lispro Pen you are using after 28 days, even if it still has insulin left in it.

General information about the safe and effective use of your Pen

- Keep your Pen and needles out of the reach of children.
- Do not use your Pen if any part looks broken or damaged.
- Always carry an extra Pen in case yours is lost or damaged.

Troubleshooting

- If you can not remove the Pen Cap, gently twist the cap back and forth, and then pull the cap straight off.
- If the Dose Knob is hard to push:
  - Pushing the Dose Knob more slowly will make it easier to inject.
  - Your Needle may be blocked. Put on a new Needle and prime the Pen.
  - You may have dust, food, or liquid inside the Pen. Throw the Pen away and get a new Pen.

If you have any questions or problems with your Insulin Lispro KwikPen, contact Lilly at 1-800-LillyRx (1-800-545-5979) or call your healthcare provider for help.

Manufactured by:
Eli Lilly and Company
Indianapolis, IN 46285, USA
US License Number 1891

This Instructions for Use has been approved by the U.S. Food and Drug Administration.

Revised: July/2023

Humalog® and KwikPen® are registered trademarks of Eli Lilly and Company.

Copyright © 2007, 2023, Eli Lilly and Company. All rights reserved.

Insulin Lispro KwikPen meets the current dose accuracy and functional requirements of ISO 11608-1.

LISKP-0006-IFU-20230721

Junior KwikPen (U-100) Instructions for Use

INSTRUCTIONS FOR USE

Insulin Lispro [IHN-soo-lihn LIYS-proh]

Junior KwikPen®

injection, for subcutaneous use

3 mL single-patient-use pen (100 units per mL)

This product is HUMALOG® (insulin lispro).

Read the Instructions for Use before you start taking Insulin Lispro and each time you get another Insulin Lispro Junior KwikPen®. There may be new information. This information does not take the place of talking to your healthcare provider about your medical condition or your treatment.

Do not share your Insulin Lispro Junior KwikPen with other people, even if the needle has been changed. You may give other people a serious infection or get a serious infection from them.

Insulin Lispro Junior KwikPen (“Pen”) is a disposable single-patient-use prefilled pen containing 300 units of Insulin Lispro.

- You can give yourself more than 1 dose from the Pen.
- Each turn of the Dose Knob dials 0.5 (½) unit of insulin. You can give from 0.5 (½) to 30 units in a single injection.
- If your dose is more than 30 units, you will need to give yourself more than 1 injection.
- The Plunger only moves a little with each injection, and you may not notice that it moves. The Plunger will only reach the end of the cartridge when you have used all 300 units in the Pen.

People who are blind or have vision problems should not use the Pen without help from a person trained to use the Pen.

How to recognize your Insulin Lispro Junior KwikPen:

- Pen color: Blue
- Dose Knob: Blue, with raised ridges on end and side
- Label: White with an orange color bar and orange-to-yellow color band

Supplies needed to give your injection:

- Insulin Lispro Junior KwikPen
- KwikPen compatible Needle (BD [Becton, Dickinson and Company] Pen Needles recommended)
- Alcohol swab
- Gauze

Preparing your Pen

- Wash your hands with soap and water.
- Check the Pen to make sure you are taking the right type of insulin. This is especially important if you use more than 1 type of insulin.
- Do not use your Pen past the expiration date printed on the Label or for more than 28 days after you first start using the Pen.
- Always use a new needle for each injection to help prevent infections and blocked needles. Do not reuse or share your needles with other people. You may give other people a serious infection or get a serious infection from them.

Step 1:

- Pull the Pen Cap straight off.
  - Do not remove the Pen Label.
- Wipe the Rubber Seal with an alcohol swab.

Step 2:

- Check the liquid in the Pen.
  Insulin Lispro should look clear and colorless. Do not use if it is cloudy, colored, or has particles or clumps in it.

Step 3:

- Select a new Needle.
- Pull off the Paper Tab from the Outer Needle Shield.

Step 4:

- Push the capped Needle straight onto the Pen and twist the Needle on until it is tight.

Step 5:

- Pull off the Outer Needle Shield. Do not throw it away.
- Pull off the Inner Needle Shield and throw it away.

Priming your Pen

Prime before each injection.

- Priming your Pen means removing the air from the Needle and Cartridge that may collect during normal use and ensures that the Pen is working correctly.
- If you do not prime before each injection, you may get too much or too little insulin.

Step 6:

- To prime your Pen, turn the Dose Knob to select 2 units.

Step 7:
• Hold your Pen with the Needle pointing up. Tap the Cartridge Holder gently to collect air bubbles at the top.

Step 8:

- Continue holding your Pen with the Needle pointing up. Push the Dose Knob in until it stops, and “0” is seen in the Dose Window. Hold the Dose Knob in and count to 5 slowly.
  You should see insulin at the tip of the Needle.
  - If you do not see insulin, repeat the priming steps 6 to 8, but not more than 4 times.
  - If you still do not see insulin, change the Needle and repeat the priming steps 6 to 8.

Small air bubbles are normal and will not affect your dose.

Selecting your dose

- You can give from 0.5 (½) to 30 units in a single injection.
- If your dose is more than 30 units, you will need to give more than 1 injection.
  - If you need help with dividing up your dose the right way, ask your healthcare provider.
  - You must use a new Needle for each injection and repeat the priming step.

Step 9:

- Turn the Dose Knob to select the number of units you need to inject. The Dose Indicator should line up with your dose.
  - The Pen dials 0.5 (½) unit at a time.
  - The Dose Knob clicks as you turn it.
  - Do not dial your dose by counting the clicks. You may dial the wrong dose. This may lead to you getting too much insulin or not enough insulin.
  - The dose can be corrected by turning the Dose Knob in either direction until the correct dose lines up with the Dose Indicator.
  - The whole unit numbers (for example, 4) are printed on the dial.
  - The half units are shown as lines between the whole unit numbers.
- Always check the number in the Dose Window to make sure you have dialed the correct dose.

Example: 4 units shown in the Dose Window
Example: 10.5 (10 ½) units shown in the Dose Window

- The Pen will not let you dial more than the number of units left in the Pen.
- If you need to inject more than the number of units left in the Pen, you may either:
  - inject the amount left in your Pen and then use a new Pen to give the rest of your dose, or
  - get a new Pen and inject the full dose.
- It is normal to see a small amount of insulin left in the Pen that you can not inject.

Giving your injection

- Inject your insulin as your healthcare provider has shown you.
- Change (rotate) your injection sites within the area you choose for each dose to reduce your risk of getting lipodystrophy (pits in skin or thickened skin) and localized cutaneous amyloidosis (skin with lumps) at the injection sites.
- Do not inject where the skin has pits, is thickened, or has lumps.
- Do not inject where the skin is tender, bruised, scaly or hard, or into scars or damaged skin.
- Do not try to change your dose while injecting.

Step 10:

- Choose your injection site.
  Insulin Lispro is injected under the skin (subcutaneously) of your stomach area, buttocks, upper legs or upper arms.
- Wipe your skin with an alcohol swab, and let your skin dry before you inject your dose.

Step 11:

- Insert the Needle into your skin.
- Push the Dose Knob all the way in.

- Continue to hold the Dose Knob in and slowly count to 5 before removing the Needle.

Do not try to inject your insulin by turning the Dose Knob. You will not receive your insulin by turning the Dose Knob.

Step 12:

- Pull the Needle out of your skin.
  - A drop of insulin at the Needle tip is normal. It will not affect your dose.
- Check the number in the Dose Window
  - If you see “0” in the Dose window, you have received the full amount you dialed.
  - If you do not see “0” in the Dose window, do not redial. Insert the Needle into your skin and finish your injection.
  - If you still do not think you received the full amount you dialed for your injection, do not start over or repeat that injection. Monitor your blood glucose as instructed by your healthcare provider.
  - If you normally need to give 2 injections for your full dose, be sure to give your second injection.

The Plunger only moves a little with each injection and you may not notice that it moves.
If you see blood after you take the Needle out of your skin, press the injection site lightly with a piece of gauze or an alcohol swab. Do not rub the area.

After your injection

Step 13:

- Carefully replace the Outer Needle Shield.

Step 14:

- Unscrew the capped Needle and throw it away (see Disposing of Pens and Needles section).
- Do not store the Pen with the Needle attached to prevent leaking, blocking the Needle, and air from entering the Pen.

Step 15:

- Replace the Pen Cap by lining up the Cap Clip with the Dose Indicator and pushing straight on.

Disposing of Pens and Needles

- The used Pen may be discarded in your household trash after you have removed the needle.
- Put your used Needles in a FDA-cleared sharps disposal container right away after use. Do not throw away (dispose of) loose needles in your household trash.
- If you do not have a FDA-cleared sharps disposal container, you may use a household container that is:
  - made of a heavy-duty plastic,
  - can be closed with a tight-fitting, puncture-resistant lid, without sharps being able to come out,
  - upright and stable during use,
  - leak-resistant, and
  - properly labeled to warn of hazardous waste inside the container.
- When your sharps disposal container is almost full, you will need to follow your community guidelines for the right way to dispose of your sharps disposal container. There may be state or local laws about how you should throw away used needles. For more information about safe sharps disposal, and for specific information about sharps disposal in the state that you live in, go to the FDA's website at: http://www.fda.gov/safesharpsdisposal
- Do not dispose of your used sharps disposal container in your household trash unless your community guidelines permit this. Do not recycle the container.

Storing your Pen

Unused Pens

- Store unused Pens in the refrigerator at 36°F to 46°F (2°C to 8°C).
- Do not freeze your insulin. Do not use if it has been frozen.
- Unused Pens may be used until the expiration date printed on the Label, if the Pen has been kept in the refrigerator.

In-use Pen

- Store the Pen you are currently using at room temperature [up to 86°F (30°C)]. Keep away from heat and light.
- Throw away the Insulin Lispro Pen you are using after 28 days, even if it still has insulin left in it.

General information about the safe and effective use of your Pen

- Keep your Pen and Needles out of the sight and reach of children.
- Do not use your Pen if any part looks broken or damaged.
- Always carry an extra Pen in case yours is lost or damaged.

Troubleshooting

- If you can not remove the Pen Cap, gently twist the cap back and forth, and then pull the cap straight off.
- If the Dose Knob is hard to push:
  - Pushing the Dose Knob more slowly will make it easier to inject.
  - Your Needle may be blocked. Put on a new Needle and prime the Pen.
  - You may have dust, food, or liquid inside the Pen. Throw the Pen away and get a new Pen.

If you have any questions or problems with your Insulin Lispro Junior KwikPen, contact Lilly at 1-800-LillyRx (1-800-545-5979) or call your healthcare provider for help.

Manufactured by:
Eli Lilly and Company
Indianapolis, IN 46285, USA
US License Number 1891

This Instructions for Use has been approved by the U.S. Food and Drug Administration.

Revised: July/2023

Humalog® and KwikPen® are registered trademarks of Eli Lilly and Company.

Copyright © 2017, 2023, Eli Lilly and Company. All rights reserved.

Insulin Lispro Junior KwikPen meets the current dose accuracy and functional requirements of ISO 11608-1.

LIS-JRKP-0002-IFU-20230721

PACKAGE CARTON – Insulin Lispro Injection 10 mL vial

NDC 0002-7737-01

Insulin Lispro Injection

100 units per mL (U-100)

For subcutaneous or intrevenous use

10 mL multiple-dose vial

Use only with a U-100 syringe

This product is Humalog.

Rx only

Lilly

PACKAGE CARTON – Insulin Lispro Injection KwikPen

NDC 0002-8222-59

Insulin Lispro KwikPen® Injection

For Single Patient Use Only

HP-8222

Dispense in this sealed carton.

Needles not included

100 units per mL (U-100)

This device is recommended for use with Becton, Dickinson and Company's insulin pen needles

For subcutaneous use only.

prefilled insulin delivery device

Rx only

This product is Humalog.

5 x 3 mL Prefilled Pens

Read Insulin Delivery Device Instructions for Use

PACKAGE CARTON – Insulin Lispro Injection Junior KwikPen

Dispense in this sealed carton.

NDC 0002-7752-05

Insulin Lispro Injection

Junior KwikPen®

For Single Patient Use Only

100 units per mL (U-100)

The pen can deliver 0.5 (½) to 30 units in one injection.

5 x 3 mL prefilled pens

For subcutaneous use only.

prefilled insulin delivery device

Rx only

This product is Humalog.

Read Insulin Lispro Injection Junior KwikPen® Instructions for Use.

NEEDLES NOT INCLUDED

This device is recommended for use with Becton, Dickinson and Company's insulin pen needles.

Lilly